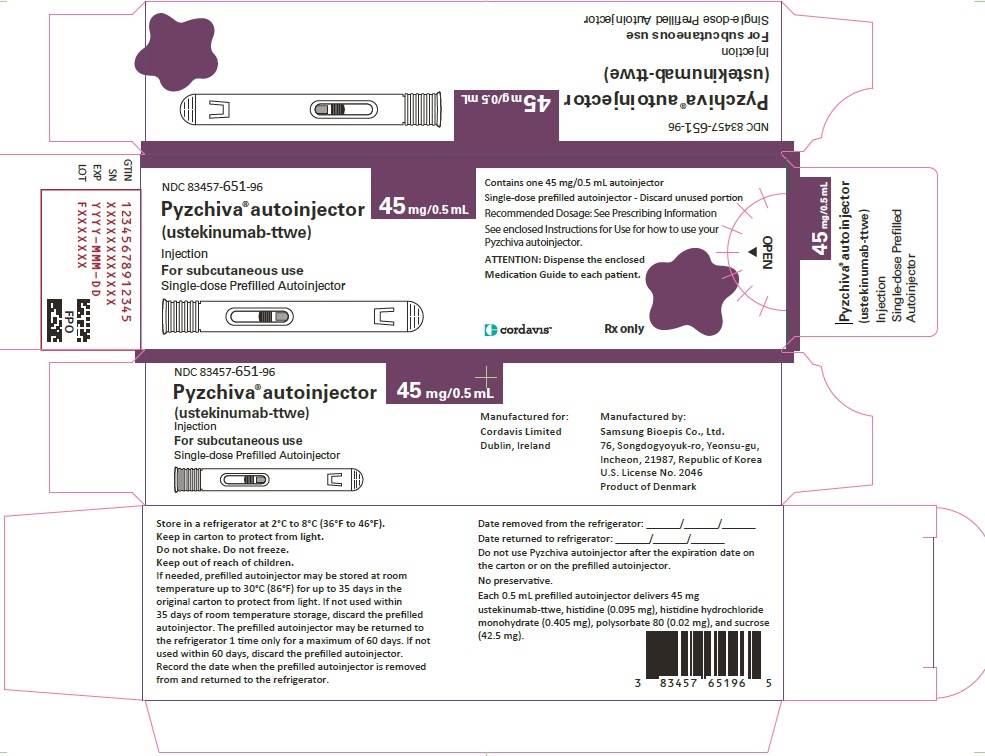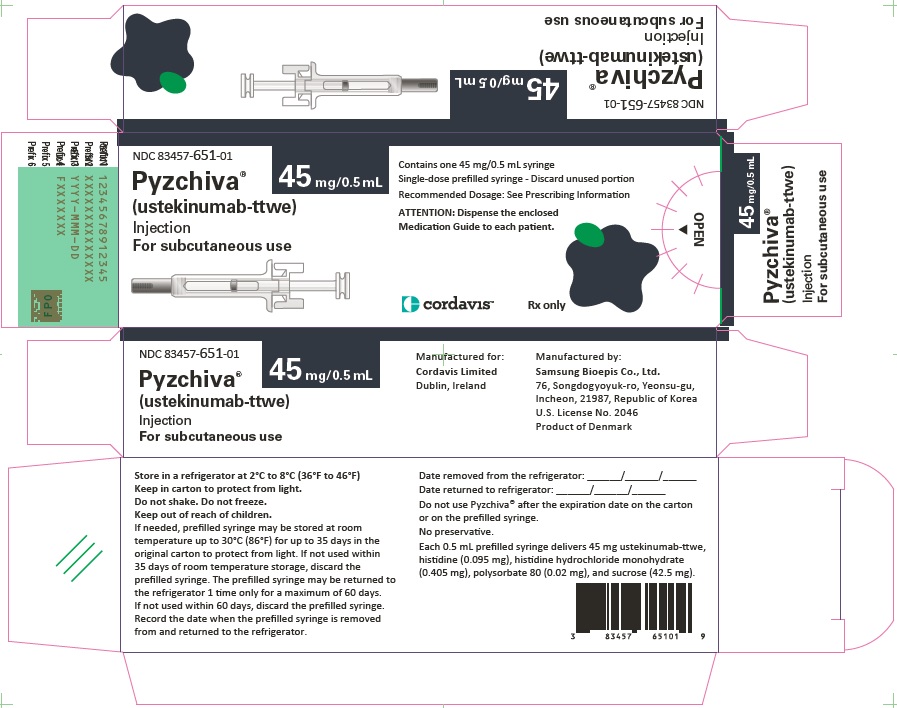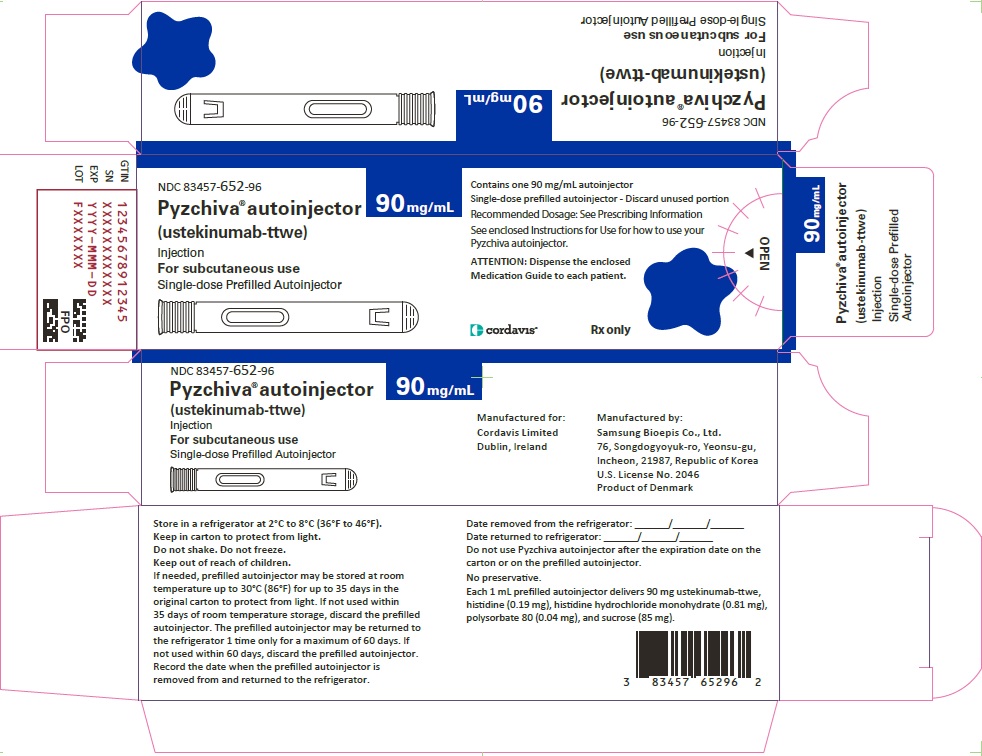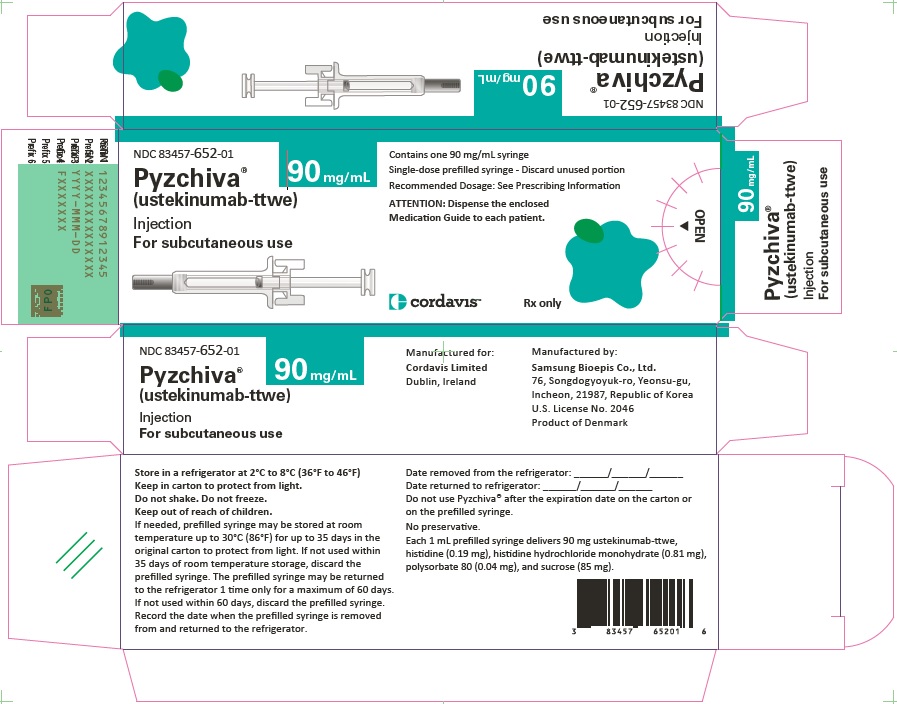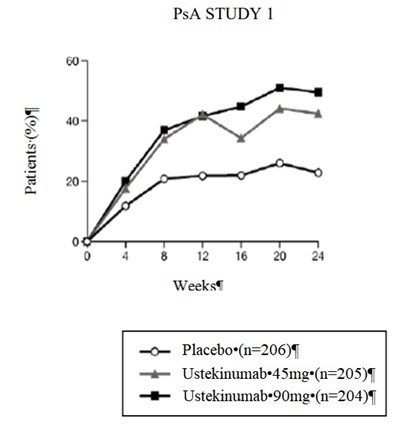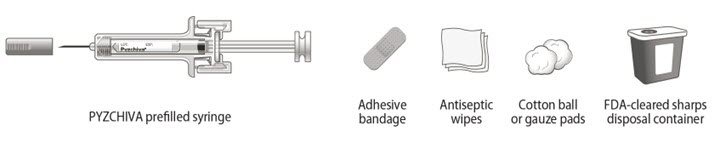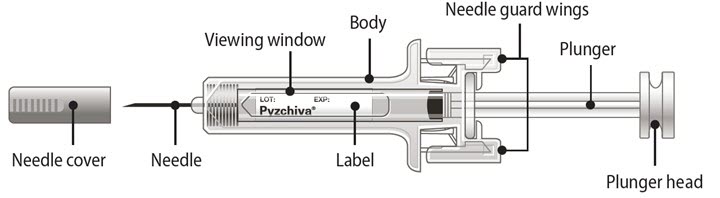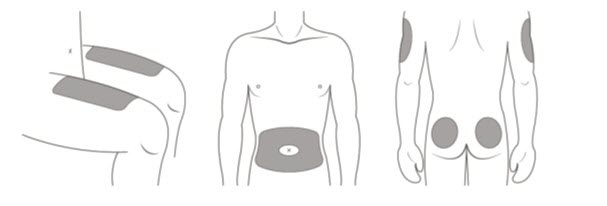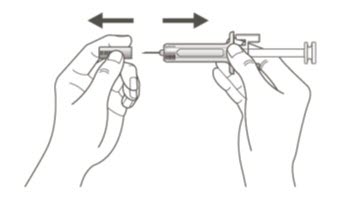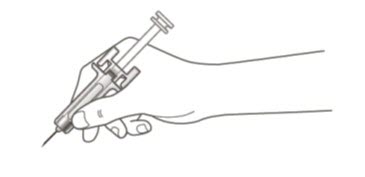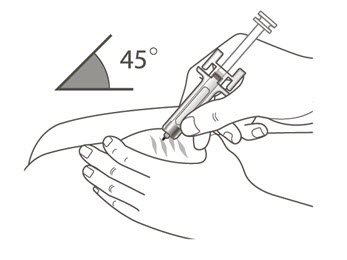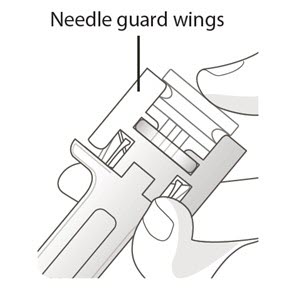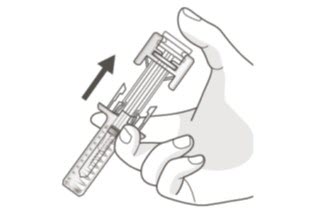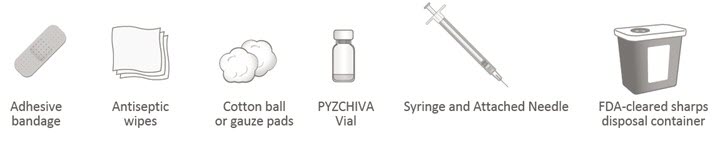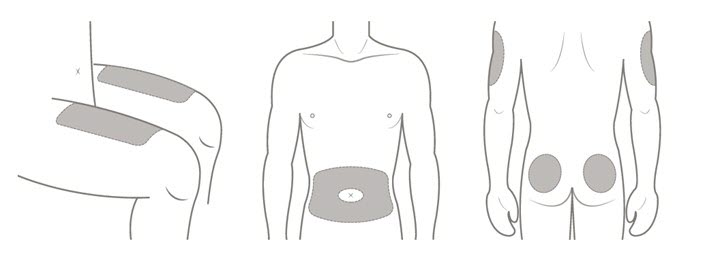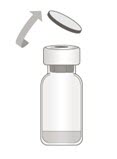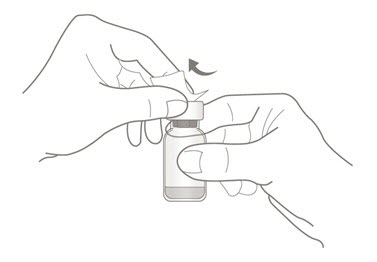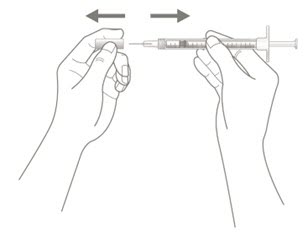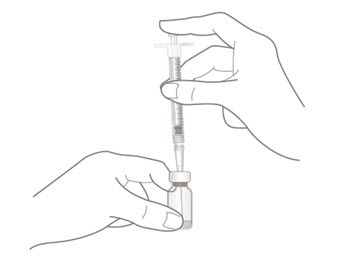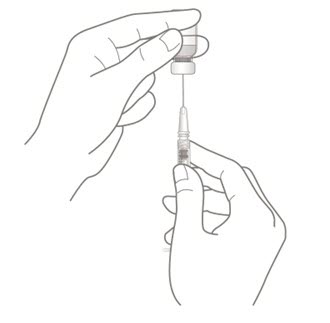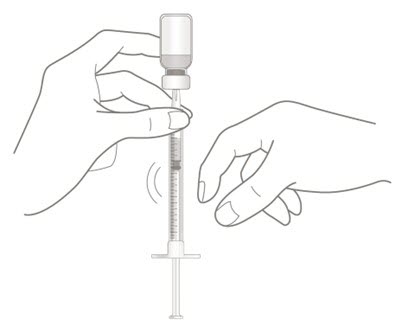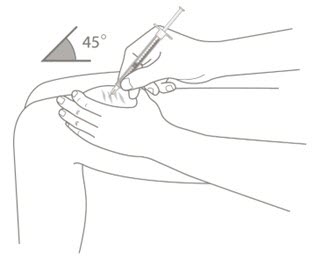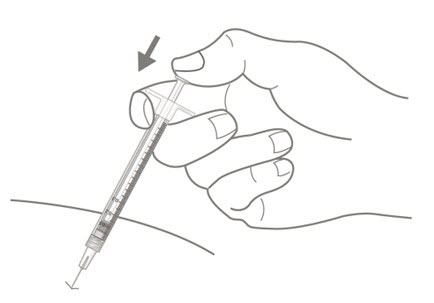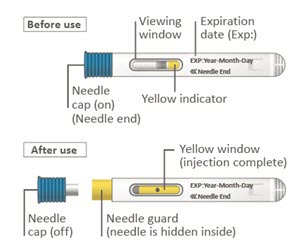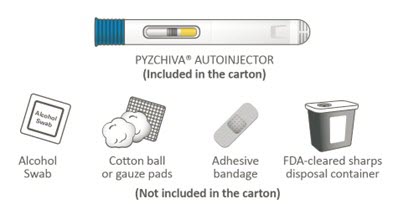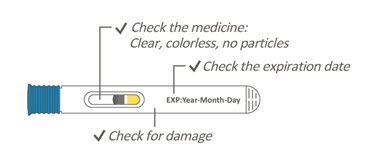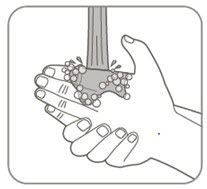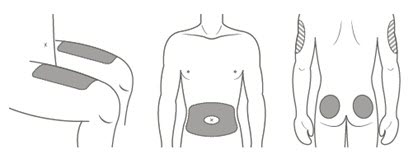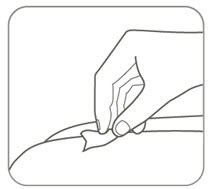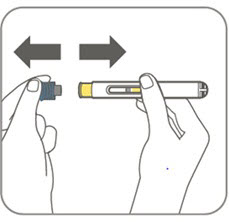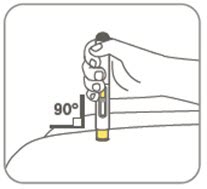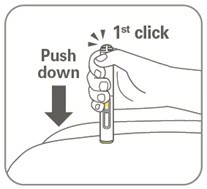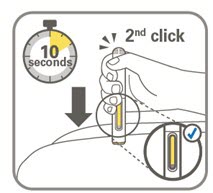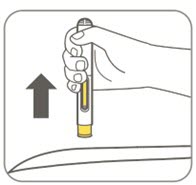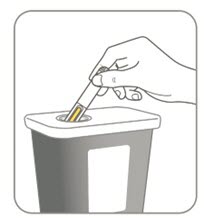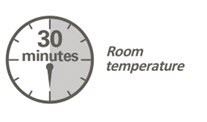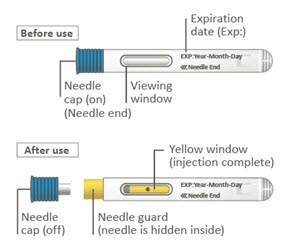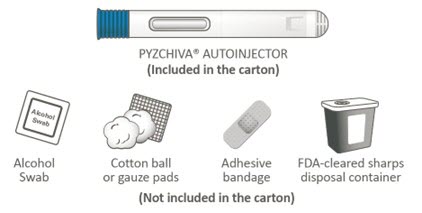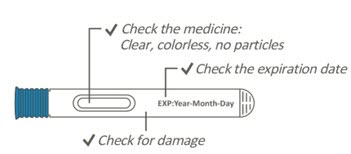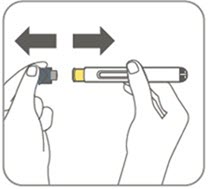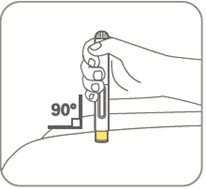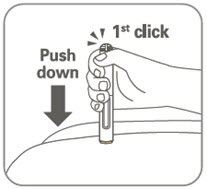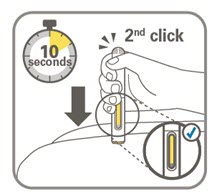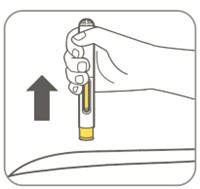 DRUG LABEL: PYZCHIVA
NDC: 83457-651 | Form: INJECTION, SOLUTION
Manufacturer: Cordavis Limited
Category: prescription | Type: HUMAN PRESCRIPTION DRUG LABEL
Date: 20260206

ACTIVE INGREDIENTS: USTEKINUMAB 45 mg/0.5 mL

HIGHLIGHTS OF PRESCRIBING INFORMATION

These highlights do not include all the information needed to use
PYZCHIVA safely and effectively. See full prescribing information for
PYZCHIVA.
PYZCHIVA® (ustekinumab-ttwe) injection, for subcutaneous or intravenous use
Initial U.S. Approval: 2024
PYZCHIVA (ustekinumab-ttwe) is biosimilar* to STELARA (ustekinumab).

RECENT MAJOR CHANGES

Warnings and Precautions,
Serious Hypersensitivity Reactions (5.5) | 02/2026

1 INDICATIONS AND USAGE

PYZCHIVA is a human interleukin-12 and -23 antagonist indicated for the treatment of:
Adult patients with:

- moderate to severe plaque psoriasis (PsO) who are candidates for phototherapy or systemic therapy. (1.1)
- active psoriatic arthritis (PsA). (1.2)
- moderately to severely active Crohn's disease (CD). (1.3)
- moderately to severely active ulcerative colitis. (1.4)

Pediatric patients 6 years and older with:

- moderate to severe plaque psoriasis (PsO), who are candidates for phototherapy or systemic therapy. (1.1)
- active psoriatic arthritis (PsA). (1.2)

2 DOSAGE AND ADMINISTRATION

Adult Patients with Plaque Psoriasis Subcutaneous Recommended Dosage (2.1):

Weight Range (kilograms) | Dosage
less than or equal to 100 kg | 45 mg administered subcutaneously initially and 4 weeks later, followed by 45 mg administered subcutaneously every 12 weeks
greater than 100 kg | 90 mg administered subcutaneously initially and 4 weeks later, followed by 90 mg administered subcutaneously every 12 weeks

Pediatric Patients 6 Years of Age and Older with Plaque Psoriasis Subcutaneous Recommended Dosage (2.1):

Weight-based dosing is recommended at the initial dose, 4 weeks later, then every 12 weeks thereafter.

Weight Range (kilograms) | Dose
less than 60 kg | 0.75 mg/kg
60 kg to 100 kg | 45 mg
greater than 100 kg | 90 mg

Psoriatic Arthritis Adult Subcutaneous Recommended Dosage (2.2):

- The recommended dosage is 45 mg administered subcutaneously initially and 4 weeks later, followed by 45 mg administered subcutaneously every 12 weeks.
- For patients with co-existent moderate-to-severe plaque psoriasis weighing greater than 100 kg, the recommended dosage is 90 mg administered subcutaneously initially and 4 weeks later, followed by 90 mg administered subcutaneously every 12 weeks.

Psoriatic Arthritis Pediatric 6 years of Age and Older Subcutaneous Recommended Dosage (2.2): Weight-based dosing is recommended at the initial dose, 4 weeks later, then every 12 weeks thereafter.

Weight Range (kilograms) | Dose
less than 60 kg | 0.75 mg/kg
60 kg or more | 45 mg
greater than 100 kg with co-existent moderate-to-severe plaque psoriasis | 90 mg

Crohn's Disease and Ulcerative Colitis Initial Adult Intravenous Recommended Dose (2.3): A single intravenous infusion using weight-based dosing:

Weight Range (kilograms) | Recommended Dose
up to 55 kg | 260 mg (2 vials)
greater than 55 kg to 85 kg | 390 mg (3 vials)
greater than 85 kg | 520 mg (4 vials)

Crohn's Disease and Ulcerative Colitis Maintenance Adult Subcutaneous Recommended Dosage (2.3): A subcutaneous 90 mg dose 8 weeks after the initial intravenous dose, then every 8 weeks thereafter.

3 DOSAGE FORMS AND STRENGTHS

Subcutaneous Injection (3)

- Injection: 45 mg/0.5 mL or 90 mg/mL solution in a single-dose prefilled syringe
- Injection: 45 mg/0.5 mL or 90 mg/mL solution in a single-dose prefilled autoinjector (PYZCHIVA AUTOINJECTOR)
- Injection: 45 mg/0.5 mL solution in a single-dose vial

Intravenous Infusion (3)

- Injection: 130 mg/26 mL (5 mg/mL) solution in a single-dose vial

4 CONTRAINDICATIONS

- Clinically significant hypersensitivity to ustekinumab products or to any of the excipients in PYZCHIVA. (4)

5 WARNINGS AND PRECAUTIONS

- Infections: Serious infections have occurred. Avoid starting PYZCHIVA during any clinically important active infection. If a serious infection or clinically significant infection develops, discontinue PYZCHIVA until the infection resolves. (5.1)
- Theoretical Risk for Particular Infections: Serious infections from mycobacteria, salmonella and Bacillus Calmette-Guerin (BCG) vaccinations have been reported in patients genetically deficient in IL-12/IL-23. Consider diagnostic tests for these infections as dictated by clinical circumstances. (5.2)
- Tuberculosis (TB): Evaluate patients for TB prior to initiating treatment with PYZCHIVA. Initiate treatment of latent TB before administering PYZCHIVA. (5.3)
- Malignancies: Ustekinumab products may increase risk of malignancy. The safety of ustekinumab products in patients with a history of or a known malignancy has not been evaluated. (5.4)
- Serious Hypersensitivity Reactions: If a severe or other clinically significant hypersensitivity reaction occurs, discontinue PYZCHIVA immediately and initiate appropriate medical treatment. (5.5)
- Posterior Reversible Encephalopathy Syndrome (PRES): If PRES is suspected, treat promptly and discontinue PYZCHIVA. (5.6)
- Immunizations: Avoid use of live vaccines in patients during treatment with PYZCHIVA. (5.7)
- Noninfectious Pneumonia: Cases of interstitial pneumonia, eosinophilic pneumonia and cryptogenic organizing pneumonia have been reported during post-approval use of ustekinumab products. If diagnosis is confirmed, discontinue PYZCHIVA and institute appropriate treatment. (5.8)

6 ADVERSE REACTIONS

Most common adverse reactions are:

- Psoriasis and Psoriatic Arthritis (≥3%): nasopharyngitis, upper respiratory tract infection, headache, and fatigue. (6.1)
- Crohn's Disease, induction (≥3%): vomiting. (6.1)
- Crohn's Disease, maintenance (≥3%): nasopharyngitis, injection site erythema, vulvovaginal candidiasis/mycotic infection, bronchitis, pruritus, urinary tract infection, and sinusitis. (6.1)
- Ulcerative colitis, induction (≥3%): nasopharyngitis (6.1)
- Ulcerative colitis, maintenance (≥3%): nasopharyngitis, headache, abdominal pain, influenza, fever, diarrhea, sinusitis, fatigue, and nausea (6.1)

To report SUSPECTED ADVERSE REACTIONS, contact Cordavis Limited at 1-833-267-3114 or FDA at 1-800-FDA-1088 or www.fda.gov/medwatch.

*Biosimilar means that the biological product is approved based on data demonstrating that it is highly similar to an FDA-approved biological product, known as a reference product, and that there are no clinically meaningful differences between the biosimilar product and the reference product. Biosimilarity of PYZCHIVA has been demonstrated for the condition(s) of use (e.g., indication(s), dosing regimen(s)), strength(s), dosage form(s), and route(s) of administration described in its Full Prescribing Information

FULL PRESCRIBING INFORMATION

1 INDICATIONS AND USAGE

1.1 Plaque Psoriasis (PsO)

PYZCHIVA is indicated for the treatment of adults and pediatric patients 6 years of age and older with moderate to severe plaque psoriasis who are candidates for phototherapy or systemic therapy.

1.2 Psoriatic Arthritis (PsA)

PYZCHIVA is indicated for the treatment of adults and pediatric patients 6 years of age and older with active psoriatic arthritis.

1.3 Crohn's Disease (CD)

PYZCHIVA is indicated for the treatment of adult patients with moderately to severely active Crohn's disease.

1.4 Ulcerative Colitis

PYZCHIVA is indicated for the treatment of adult patients with moderately to severely active ulcerative colitis.

2 DOSAGE AND ADMINISTRATION

2.1 Recommended Dosage in Plaque Psoriasis

Subcutaneous Adult Dosage Regimen

- For patients weighing 100 kg or less, the recommended dosage is 45 mg initially and 4 weeks later, followed by 45 mg every 12 weeks.
- For patients weighing more than 100 kg, the recommended dosage is 90 mg initially and 4 weeks later, followed by 90 mg every 12 weeks.

In subjects weighing more than 100 kg, 45 mg was also shown to be efficacious. However, 90 mg resulted in greater efficacy in these subjects [see Clinical Studies (14)].

Subcutaneous Pediatric Dosage Regimen

Administer PYZCHIVA subcutaneously at Weeks 0 and 4, then every 12 weeks thereafter.

The recommended dose of PYZCHIVA for pediatric patients 6 years of age and older with plaque psoriasis based on body weight is shown below (Table 1).

Table 1: Recommended Dose of PYZCHIVA for Subcutaneous Injection in Pediatric Patients 6 Years of Age and Older with Plaque Psoriasis
Body Weight of Patient at the Time of Dosing | Recommended Dose
less than 60 kg | 0.75 mg/kg
60 kg to 100 kg | 45 mg
more than 100 kg | 90 mg

For pediatric patients weighing less than 60 kg, the administration volume for the recommended dose (0.75 mg/kg) is shown in Table 2; withdraw the appropriate volume from the vial.

Table 2: Injection Volumes of PYZCHIVA 45 mg/0.5 mL Vials for Pediatric Patients 6 Years of Age and Older with Plaque Psoriasis and Pediatric Patients 6 Years of Age and Older with Psoriatic Arthritis* Weighing Less Than 60 kg
Body Weight (kg) at the time of dosing | Dose (mg) | Volume of injection (mL)
15 | 11.3 | 0.12
16 | 12 | 0.13
17 | 12.8 | 0.14
18 | 13.5 | 0.15
19 | 14.3 | 0.16
20 | 15 | 0.17
21 | 15.8 | 0.17
22 | 16.5 | 0.18
23 | 17.3 | 0.19
24 | 18 | 0.20
25 | 18.8 | 0.21
26 | 19.5 | 0.22
27 | 20.3 | 0.22
28 | 21 | 0.23
29 | 21.8 | 0.24
30 | 22.5 | 0.25
31 | 23.3 | 0.26
32 | 24 | 0.27
33 | 24.8 | 0.27
34 | 25.5 | 0.28
35 | 26.3 | 0.29
36 | 27 | 0.30
37 | 27.8 | 0.31
38 | 28.5 | 0.32
39 | 29.3 | 0.32
40 | 30 | 0.33
41 | 30.8 | 0.34
42 | 31.5 | 0.35
43 | 32.3 | 0.36
44 | 33 | 0.37
45 | 33.8 | 0.37
46 | 34.5 | 0.38
47 | 35.3 | 0.39
48 | 36 | 0.40
49 | 36.8 | 0.41
50 | 37.5 | 0.42
51 | 38.3 | 0.42
52 | 39 | 0.43
53 | 39.8 | 0.44
54 | 40.5 | 0.45
55 | 41.3 | 0.46
56 | 42 | 0.46
57 | 42.8 | 0.47
58 | 43.5 | 0.48
59 | 44.3 | 0.49

* Refer to 2.2 Psoriatic Arthritis; Subcutaneous Pediatric Dosage Regimen.

2.2 Recommended Dosage in Psoriatic Arthritis

Subcutaneous Adult Dosage Regimen

- The recommended dosage is 45 mg initially and 4 weeks later, followed by 45 mg every 12 weeks.
- For patients with co-existent moderate-to-severe plaque psoriasis weighing more than 100 kg, the recommended dosage is 90 mg initially and 4 weeks later, followed by 90 mg every 12 weeks.

Subcutaneous Pediatric Dosage Regimen

Administer PYZCHIVA subcutaneously at Weeks 0 and 4, then every 12 weeks thereafter.

The recommended dose of PYZCHIVA for pediatric patients 6 years of age and older with psoriatic arthritis, based on body weight, is shown below (Table 3).

Table 3: Recommended Dose of PYZCHIVA for Subcutaneous Injection in Pediatric Patients 6 Years of Age and Older with Psoriatic Arthritis
Body Weight of Patient at the Time of Dosing | Recommended Dose
less than 60 kg* | 0.75 mg/kg
60 kg or more | 45 mg
greater than 100 kg with co-existent moderate-to-severe plaque psoriasis | 90 mg

* For pediatric patients weighing less than 60 kg, the administration volume for the recommended dose (0.75 mg/kg) is shown in Table 2; withdraw the appropriate volume from the vial.

2.3 Recommended Dosage in Crohn's Disease and Ulcerative Colitis

Intravenous Induction Adult Dosage Regimen

A single intravenous infusion dose of PYZCHIVA using the weight-based dosage regimen specified in Table 4 [see Dosage and Administration (2.5)].

Table 4: Initial Intravenous Dosage of PYZCHIVA
Body Weight of Patient at the time of dosing | Dose | Number of 130 mg/26 mL (5 mg/mL) PYZCHIVA vials
55 kg or less | 260 mg | 2
more than 55 kg to 85 kg | 390 mg | 3
more than 85 kg | 520 mg | 4

Subcutaneous Maintenance Adult Dosage Regimen

The recommended maintenance dosage is a subcutaneous 90 mg dose administered 8 weeks after the initial intravenous dose, then every 8 weeks thereafter.

2.4 General Considerations for Administration

- PYZCHIVA is intended for use under the guidance and supervision of a healthcare provider. PYZCHIVA should only be administered to patients who will be closely monitored and have regular follow-up visits with a healthcare provider. The appropriate dose should be determined by a healthcare provider using the patient's current weight at the time of dosing. In pediatric patients, it is recommended that PYZCHIVA be administered by a healthcare provider. If a healthcare provider determines that it is appropriate, a patient may self-inject or a caregiver may inject PYZCHIVA after proper training in subcutaneous injection technique. Instruct patients to follow the directions provided in the Instructions for Use [see Instructions for Use].
- It is recommended that each injection be administered at a different anatomic location (such as upper arms, gluteal regions, thighs, or any quadrant of abdomen) than the previous injection, and not into areas where the skin is tender, bruised, erythematous, or indurated. When using the vial, a 1 mL syringe with a 27 gauge, ½ inch needle is recommended.
- Prior to administration, visually inspect PYZCHIVA for particulate matter and discoloration. PYZCHIVA is a clear, colorless to light yellow, sterile and preservative-free solution. Do not use PYZCHIVA if it is discolored or cloudy, or if other particulate matter is present. PYZCHIVA does not contain preservatives; therefore, discard any unused product remaining in the vial, syringe and/or PYZCHIVA AUTOINJECTOR.

2.5 Preparation and Administration of PYZCHIVA 130 mg/26 mL (5 mg/mL) Vial for Intravenous Infusion (Crohn's Disease and Ulcerative Colitis)

PYZCHIVA solution for intravenous infusion must be diluted, prepared and infused by a healthcare professional using aseptic technique.

1. Calculate the dose and the number of PYZCHIVA vials needed based on patient weight (Table 4). Each 26 mL vial of PYZCHIVA contains 130 mg of ustekinumab-ttwe.
2. Withdraw, and then discard a volume of the 0.9% Sodium Chloride Injection, USP from the 250 mL infusion bag equal to the volume of PYZCHIVA to be added (discard 26 mL sodium chloride for each vial of PYZCHIVA needed, for 2 vials- discard 52 mL, for 3 vials- discard 78 mL, 4 vials- discard 104 mL). Alternatively, a 250 mL infusion bag containing 0.45% Sodium Chloride Injection, USP may be used.
3. Withdraw 26 mL of PYZCHIVA from each vial needed and add it to the 250 mL infusion bag. The final volume in the infusion bag should be 250 mL. Gently mix. Protect from light.
4. Visually inspect the diluted solution before infusion. Do not use if visibly opaque particles, discoloration or foreign particles are observed.
5. Infuse the diluted solution over a period of at least one hour. Once diluted in the infusion bag, the infusion should be completely administered within 36 hours at room temperature up to 30°C (86°F) .
6. Use only an infusion set with an in-line, sterile, non-pyrogenic, low protein-binding filter (pore size 0.2 micrometer).
7. Do not infuse PYZCHIVA concomitantly in the same intravenous line with other agents.
8. PYZCHIVA does not contain preservatives. Each vial is for one-time use in only one patient. Discard any remaining solution. Dispose any unused medicinal product in accordance with local requirements.

Storage

- The diluted infusion solution may be kept at room temperature up to 30°C (86°F) for up to 36 hours including infusion period.
- If necessary, the diluted infusion solution may be stored refrigerated at 2°C to 8°C (36°F to 46°F) for up to 15 days. After removal from refrigeration, the diluted solution may be stored at room temperature at up to 30°C (86°F) for an additional 24 hours including infusion period. Storage time at refrigerated or room temperature begins once the diluted solution has been prepared. Do not freeze. Protect from light. Discard any unused portion of the infusion solution.

3 DOSAGE FORMS AND STRENGTHS

PYZCHIVA (ustekinumab-ttwe) is a clear, colorless to light yellow, sterile and preservative-free solution.

Subcutaneous Injection

- Injection: 45 mg/0.5 mL or 90 mg/mL solution in a single-dose prefilled syringe
- Injection: 45 mg/0.5 mL or 90 mg/mL solution in a single-dose prefilled autoinjector (PYZCHIVA AUTOINJECTOR)
- Injection: 45 mg/0.5 mL solution in a single-dose vial

Intravenous Infusion

- Injection: 130 mg/26 mL (5 mg/mL) solution in a single-dose vial

4 CONTRAINDICATIONS

PYZCHIVA is contraindicated in patients with clinically significant hypersensitivity to ustekinumab products or to any of the excipients in PYZCHIVA [see Warnings and Precautions (5.5)].

5 WARNINGS AND PRECAUTIONS

5.1 Infections

Ustekinumab products may increase the risk of infections and reactivation of latent infections. Serious bacterial, mycobacterial, fungal, and viral infections were observed in patients receiving ustekinumab products [see Adverse Reactions (6.1, 6.3)].

Serious infections requiring hospitalization, or otherwise clinically significant infections, reported in clinical trials included the following:

- Plaque Psoriasis: diverticulitis, cellulitis, pneumonia, appendicitis, cholecystitis, sepsis, osteomyelitis, viral infections, gastroenteritis and urinary tract infections.
- Psoriatic arthritis: cholecystitis.
- Crohn's disease: anal abscess, gastroenteritis, ophthalmic herpes zoster, pneumonia, and listeria meningitis.
- Ulcerative colitis: gastroenteritis, ophthalmic herpes zoster, pneumonia, and listeriosis.

Avoid initiating treatment with PYZCHIVA in patients with any clinically important active infection until the infection resolves or is adequately treated. Consider the risks and benefits of treatment prior to initiating use of PYZCHIVA in patients with a chronic infection or a history of recurrent infection.

Instruct patients to seek medical advice if signs or symptoms suggestive of an infection occur while on treatment with PYZCHIVA and discontinue PYZCHIVA for serious or clinically significant infections until the infection resolves or is adequately treated.

5.2 Theoretical Risk for Vulnerability to Particular Infections

Individuals genetically deficient in IL-12/IL-23 are particularly vulnerable to disseminated infections from mycobacteria (including nontuberculous, environmental mycobacteria), salmonella (including nontyphi strains), and Bacillus Calmette-Guerin (BCG) vaccinations. Serious infections and fatal outcomes have been reported in such patients.

It is not known whether patients with pharmacologic blockade of IL-12/IL-23 from treatment with ustekinumab products may be susceptible to these types of infections. Consider appropriate diagnostic testing (e.g., tissue culture, stool culture, as dictated by clinical circumstances).

5.3 Pre-treatment Evaluation for Tuberculosis

Evaluate patients for tuberculosis infection prior to initiating treatment with PYZCHIVA.

Avoid administering PYZCHIVA to patients with active tuberculosis infection. Initiate treatment of latent tuberculosis prior to administering PYZCHIVA. Consider anti-tuberculosis therapy prior to initiation of PYZCHIVA in patients with a past history of latent or active tuberculosis in whom an adequate course of treatment cannot be confirmed. Closely monitor patients receiving PYZCHIVA for signs and symptoms of active tuberculosis during and after treatment.

5.4 Malignancies

Ustekinumab products are immunosuppressants and may increase the risk of malignancy. Malignancies were reported among subjects who received ustekinumab in clinical trials [see Adverse Reactions (6.1)]. In rodent models, inhibition of IL-12/IL-23p40 increased the risk of malignancy [see Nonclinical Toxicology (13)].

The safety of ustekinumab products has not been evaluated in patients who have a history of malignancy or who have a known malignancy.
There have been post-marketing reports of the rapid appearance of multiple cutaneous squamous cell carcinomas in patients receiving ustekinumab products who had pre-existing risk factors for developing non-melanoma skin cancer. Monitor all patients receiving PYZCHIVA for the appearance of non-melanoma skin cancer. Closely follow patients greater than 60 years of age, those with a medical history of prolonged immunosuppressant therapy and those with a history of PUVA treatment [see Adverse Reactions (6.1)].

5.5 Serious Hypersensitivity Reactions

Serious hypersensitivity reactions, including anaphylaxis and angioedema, have been reported with ustekinumab products in clinical trials and postmarketing. Some serious hypersensitivity reactions have occurred during the first intravenous dose of ustekinumab products [see Adverse Reactions (6.1, 6.3)].

If a severe or clinically significant hypersensitivity reaction occurs, discontinue PYZCHIVA immediately and initiate appropriate medical treatment [see Contraindications (4)].

5.6 Posterior Reversible Encephalopathy Syndrome (PRES)

Two cases of posterior reversible encephalopathy syndrome (PRES), also known as Reversible Posterior Leukoencephalopathy Syndrome (RPLS), were reported in clinical trials. Cases have also been reported in postmarketing experience in patients with psoriasis, psoriatic arthritis and Crohn's disease. Clinical presentation included headaches, seizures, confusion, visual disturbances, and imaging changes consistent with PRES a few days to several months after ustekinumab product initiation. A few cases reported latency of a year or longer. Patients recovered with supportive care following withdrawal of ustekinumab products.

Monitor all patients treated with PYZCHIVA for signs and symptoms of PRES. If PRES is suspected, promptly administer appropriate treatment and discontinue PYZCHIVA.

5.7 Immunizations

Prior to initiating therapy with PYZCHIVA, patients should receive all age-appropriate immunizations as recommended by current immunization guidelines. Patients being treated with PYZCHIVA should avoid receiving live vaccines. Avoid administering BCG vaccines during treatment with PYZCHIVA or for one year prior to initiating treatment or one year following discontinuation of treatment. Caution is advised when administering live vaccines to household contacts of patients receiving PYZCHIVA because of the potential risk for shedding from the household contact and transmission to patient.

Non-live vaccinations received during a course of PYZCHIVA may not elicit an immune response sufficient to prevent disease.

5.8 Noninfectious Pneumonia

Cases of interstitial pneumonia, eosinophilic pneumonia and cryptogenic organizing pneumonia have been reported during post-approval use of ustekinumab products. Clinical presentations included cough, dyspnea, and interstitial infiltrates following one to three doses. Serious outcomes have included respiratory failure and prolonged hospitalization. Patients improved with discontinuation of therapy and in certain cases administration of corticosteroids. If diagnosis is confirmed, discontinue PYZCHIVA and institute appropriate treatment [see Adverse Reactions (6.3)].

6 ADVERSE REACTIONS

The following serious adverse reactions are discussed elsewhere in the label:

- Infections [see Warnings and Precautions (5.1)]
- Malignancies [see Warnings and Precautions (5.4)]
- Serious Hypersensitivity Reactions [see Warnings and Precautions (5.5)]
- Posterior Reversible Encephalopathy Syndrome (PRES) [see Warnings and Precautions (5.6)]
- Noninfectious Pneumonia [see Warnings and Precautions (5.8)]

6.1 Clinical Trials Experience

Because clinical trials are conducted under widely varying conditions, adverse reaction rates observed in the clinical trials of a drug cannot be directly compared to rates in the clinical trials of another drug and may not reflect the rates observed in practice.

Adult Subjects with Plaque Psoriasis

The safety data reflect exposure to ustekinumab in 3117 adult subjects with plaque psoriasis, including 2414 exposed for at least 6 months, 1855 exposed for at least one year, 1653 exposed for at least two years, 1569 exposed for at least three years, 1482 exposed for at least four years and 838 exposed for at least five years.

Table 5 summarizes the adverse reactions that occurred at a rate of at least 1% with higher rates in the ustekinumab groups during the placebo-controlled period of Ps STUDY 1 and Ps STUDY 2 [see Clinical Studies (14)].

Table 5: Adverse Reactions Reported by ≥1% of Subjects with Plaque Psoriasis and at Higher Rates in the Ustekinumab Groups through Week 12 in Ps STUDY 1 and Ps STUDY 2
 |  | Ustekinumab
 | Placebo | 45 mg | 90 mg
Subjects treated | 665 | 664 | 666
Nasopharyngitis | 51 (8%) | 56 (8%) | 49 (7%)
Upper respiratory tract infection | 30 (5%) | 36 (5%) | 28 (4%)
Headache | 23 (3%) | 33 (5%) | 32 (5%)
Fatigue | 14 (2%) | 18 (3%) | 17 (3%)
Back pain | 8 (1%) | 9 (1%) | 14 (2%)
Dizziness | 8 (1%) | 8 (1%) | 14 (2%)
Pharyngolaryngeal pain | 7 (1%) | 9 (1%) | 12 (2%)
Pruritus | 9 (1%) | 10 (2%) | 9 (1%)
Injection site erythema | 3 (<1%) | 6 (1%) | 13 (2%)
Myalgia | 4 (1%) | 7 (1%) | 8 (1%)
Depression | 3 (<1%) | 8 (1%) | 4 (1%)

Adverse reactions that occurred at rates less than 1% in the controlled period of Ps STUDIES 1 and 2 through week 12 included: cellulitis, herpes zoster, diverticulitis and certain injection site reactions (pain, swelling, pruritus, induration, hemorrhage, bruising, and irritation).

One case of PRES occurred during clinical trials in adult subjects with plaque psoriasis [see Warnings and Precautions (5.6)].

Infections

In the placebo-controlled period of clinical trials of subjects with plaque psoriasis (average follow-up of 12.6 weeks for subjects receiving placebo and 13.4 weeks for ustekinumab-treated subjects), 27% of ustekinumab-treated subjects reported infections (1.39 per patient-years of follow-up) compared with 24% of subjects receiving placebo (1.21 per patient-years of follow-up). Serious infections occurred in 0.3% of ustekinumab-treated subjects (0.01 per patient-years of follow-up) and in 0.4% of subjects receiving placebo (0.02 per patient-year of follow-up) [see Warnings and Precautions (5.1)].

In the controlled and non-controlled portions of clinical trials in subjects with plaque psoriasis (median follow-up of 3.2 years), representing 8998 patient-years of exposure, 72.3% of ustekinumab-treated subjects reported infections (0.87 per patient-years of follow-up). Serious infections were reported in 2.8% of subjects (0.01 per patient-years of follow-up).

Malignancies

In the controlled and non-controlled portions of clinical trials in subjects with plaque psoriasis (median follow-up of 3.2 years, representing 8998 patient-years of exposure), 1.7% of ustekinumab-treated subjects reported malignancies excluding non-melanoma skin cancers (0.60 per hundred patient-years of follow-up). Non-melanoma skin cancer was reported in 1.5% of ustekinumab-treated subjects (0.52 per hundred patient-years of follow-up) [see Warnings and Precautions (5.4)]. The most frequently observed malignancies other than non-melanoma skin cancer during the clinical trials were: prostate, melanoma, colorectal and breast. Malignancies other than non-melanoma skin cancer in ustekinumab-treated subjects during the controlled and uncontrolled portions of trials were similar in type and number to what would be expected in the general U.S. population according to the SEER database (adjusted for age, gender and race).^1

Pediatric Subjects with Plaque Psoriasis

The safety of ustekinumab was assessed in two trials of pediatric subjects with moderate to severe plaque psoriasis. Ps STUDY 3 evaluated safety for up to 60 weeks in 110 pediatric subjects 12 to 17 years old. Ps STUDY 4 evaluated safety for up to 56 weeks in 44 pediatric subjects 6 to 11 years old. The safety profile in pediatric subjects was similar to the safety profile from trials in adults with plaque psoriasis.

Psoriatic Arthritis

The safety of ustekinumab was assessed in 927 subjects in two randomized, double-blind, placebo-controlled trials in adults with active psoriatic arthritis (PsA). The overall safety profile of ustekinumab in subjects with PsA was consistent with the safety profile seen in clinical trials in adult subjects with plaque psoriasis. A higher incidence of arthralgia, nausea, and dental infections was observed in ustekinumab-treated subjects when compared with placebo- treated subjects (3% vs. 1% for arthralgia and 3% vs. 1% for nausea; 1% vs. 0.6% for dental infections) in the placebo-controlled portions of the PsA clinical trials.

Crohn's Disease

The safety of ustekinumab was assessed in 1407 subjects with moderately to severely active Crohn's disease (Crohn's Disease Activity Index [CDAI] greater than or equal to 220 and less than or equal to 450) in three randomized, double-blind, placebo-controlled, parallel-group, multicenter trials. These 1407 subjects included 40 subjects who received a prior investigational intravenous ustekinumab formulation but were not included in the efficacy analyses. In trials CD-1 and CD-2 there were 470 subjects who received ustekinumab 6 mg/kg as a weight-based single intravenous induction dose and 466 who received placebo [see Dosage and Administration (2.3)]. Subjects who were responders in either trial CD-1 or CD-2 were randomized to receive a subcutaneous maintenance regimen of either 90 mg ustekinumab every 8 weeks, or placebo for 44 weeks in trial CD-3. Subjects in these 3 trials may have received other concomitant therapies including aminosalicylates, immunomodulatory agents [azathioprine (AZA), 6- mercaptopurine (6-MP), methotrexate (MTX)], oral corticosteroids (prednisone or budesonide), and/or antibiotics for their Crohn's disease [see Clinical Studies (14.4)].

The overall safety profile of ustekinumab was consistent with the safety profile seen in the clinical trials in adult subjects with plaque psoriasis and psoriatic arthritis. Common adverse reactions in trials CD-1 and CD-2 and in trial CD-3 are listed in Table 6 and Table 7, respectively.

Table 6: Common Adverse Reactions Through Week 8 in Trials CD-1 and CD-2 occurring in ≥3% of Ustekinumab-Treated Subjects and Higher Than Subjects Receiving Placebo
 | Placebo N=466 | Ustekinumab 6 mg/kg single intravenous induction dose N=470
Vomiting | 3% | 4%

Other less common adverse reactions reported in subjects in trials CD-1 and CD-2 included asthenia (1% vs 0.4%), acne (1% vs 0.4%), and pruritus (2% vs 0.4%).

Table 7: Common Adverse Reactions Through Week 44 in Trial CD-3 Occurring in ≥3% of Ustekinumab-Treated Subjects and Higher Than Subjects Receiving Placebo
 | Placebo N=133 | Ustekinumab 90 mg subcutaneous maintenance dose every 8 weeks N=131
Nasopharyngitis | 8% | 11%
Injection site erythema | 0 | 5%
Vulvovaginal candidiasis/mycotic infection | 1% | 5%
Bronchitis | 3% | 5%
Pruritus | 2% | 4%
Urinary tract infection | 2% | 4%
Sinusitis | 2% | 3%

Infections

In subjects with Crohn's disease, serious or other clinically significant infections included anal abscess, gastroenteritis, and pneumonia. In addition, listeria meningitis and ophthalmic herpes zoster were reported in one subject each [see Warnings and Precautions (5.1)].

Malignancies

With up to one year of treatment in the Crohn's disease clinical trials, 0.2% of ustekinumab-treated subjects (0.36 events per hundred patient-years) and 0.2% of placebo-treated subjects (0.58 events per hundred patient-years) developed non- melanoma skin cancer. Malignancies other than non-melanoma skin cancers occurred in 0.2% of ustekinumab-treated subjects (0.27 events per hundred patient-years) and in none of the placebo-treated subjects.

Hypersensitivity Reactions Including Anaphylaxis

In CD trials, two subjects reported hypersensitivity reactions following ustekinumab administration. One subject experienced signs and symptoms consistent with anaphylaxis (tightness of the throat, shortness of breath, and flushing) after a single subcutaneous administration (0.1% of subjects receiving subcutaneous ustekinumab). In addition, one subject experienced signs and symptoms consistent with or related to a hypersensitivity reaction (chest discomfort, flushing, urticaria, and increased body temperature) after the initial intravenous ustekinumab dose (0.08% of subjects receiving intravenous ustekinumab). These subjects were treated with oral antihistamines or corticosteroids and in both cases symptoms resolved within an hour [see Warnings and Precautions (5.5)].

Ulcerative Colitis

The safety of ustekinumab was evaluated in two randomized, double-blind, placebo- controlled clinical trials (UC-1 [IV induction] and UC-2 [SC maintenance]) in 960 adult subjects with moderately to severely active ulcerative colitis [see Clinical Studies (14.5)]. The overall safety profile of ustekinumab in subjects with ulcerative colitis was consistent with the safety profile seen across all approved indications. Adverse reactions reported in at least 3% of ustekinumab-treated subjects and at a higher rate than placebo were:

- Induction (UC-1): nasopharyngitis (7% vs 4%).
- Maintenance (UC-2): nasopharyngitis (24% vs 20%), headache (10% vs 4%), abdominal pain (7% vs 3%), influenza (6% vs 5%), fever (5% vs. 4%), diarrhea (4% vs 1%), sinusitis (4% vs 1%), fatigue (4% vs 2%), and nausea (3% vs 2%).

Infections

In subjects with ulcerative colitis, serious or other clinically significant infections included gastroenteritis and pneumonia. In addition, listeriosis and ophthalmic herpes zoster were reported in one subject each [see Warnings and Precautions (5.1)].

Malignancies

With up to one year of treatment in the ulcerative colitis clinical trials, 0.4% of ustekinumab-treated subjects (0.48 events per hundred patient-years) and 0.0% of subjects receiving placebo (0.00 events per hundred patient-years) developed non- melanoma skin cancer. Malignancies other than non-melanoma skin cancers occurred in 0.5% of ustekinumab-treated subjects (0.64 events per hundred patient-years) and 0.2% of subjects receiving placebo (0.40 events per hundred patient-years).

6.2 Immunogenicity

The observed incidence of anti-drug antibodies is highly dependent on the sensitivity and specificity of the assay. Differences in assay methods preclude meaningful comparisons of the incidence of anti-drug antibodies in the studies described below with the incidence of anti-drug antibodies in other studies, including those of ustekinumab or of other ustekinumab products. Approximately 6 to 12.4% of subjects treated with ustekinumab in clinical trials in subjects with plaque psoriasis and psoriatic arthritis developed antibodies to ustekinumab, which were generally low-titer. In clinical trials in subjects with plaque psoriasis, antibodies to ustekinumab were associated with reduced or undetectable serum ustekinumab concentrations and reduced efficacy. In trials in subjects with plaque psoriasis, the majority of subjects who were positive for antibodies to ustekinumab had neutralizing antibodies.

In clinical trials in subjects with Crohn's disease and ulcerative colitis, 2.9% and 4.6% of subjects, respectively, developed antibodies to ustekinumab when treated with ustekinumab for approximately one year. No apparent association between the development of antibodies to ustekinumab and the development of injection site reactions was seen.

6.3 Postmarketing Experience

The following adverse reactions have been reported during post-approval use of ustekinumab products. Because these reactions are reported voluntarily from a population of uncertain size, it is not always possible to reliably estimate their frequency or establish a causal relationship to ustekinumab product exposure.

Immune system disorders: Hypersensitivity reactions (e.g., anaphylaxis, angioedema, dyspnea, rash, urticaria), including a fatal case that presented with chest tightness and dyspnea during infusion of the first dose.

Infections and infestations: Lower respiratory tract infection (including opportunistic fungal infections and tuberculosis).

Neurological disorders: Posterior Reversible Encephalopathy Syndrome (PRES).

Respiratory, thoracic and mediastinal disorders: Interstitial pneumonia, eosinophilic pneumonia and cryptogenic organizing pneumonia.

Skin reactions: Pustular psoriasis, erythrodermic psoriasis, hypersensitivity vasculitis.

7 DRUG INTERACTIONS

7.1 Concomitant Therapies

In trials in subjects with plaque psoriasis the safety of ustekinumab products in combination with immunosuppressive agents or phototherapy has not been evaluated. In trials in subjects with psoriatic arthritis, concomitant MTX use did not appear to influence the safety or efficacy of ustekinumab. In trials in subjects with Crohn's disease (CD-1 and CD-2) and ulcerative colitis (UC-1), immunomodulators (6-MP, AZA, MTX) were used concomitantly in approximately 30% of subjects and corticosteroids were used concomitantly in approximately 40% and 50% of Crohn's disease and ulcerative colitis subjects, respectively. Use of these concomitant therapies did not appear to influence the overall safety or efficacy of ustekinumab.

7.2 CYP450 Substrates

The formation of CYP450 enzymes can be suppressed by increased levels of certain cytokines (e.g., IL-1, IL-6, TNFα, IFN) during chronic inflammation. Thus, use of ustekinumab products, antagonists of IL-12 and IL-23, could normalize the formation of CYP450 enzymes. Upon initiation or discontinuation of PYZCHIVA in patients who are receiving concomitant CYP450 substrates, particularly those with a narrow therapeutic index, consider monitoring for therapeutic effect or drug concentration and adjust the individual dosage of the CYP substrate as needed. See the prescribing information of specific CYP substrates.

A CYP-mediated drug interaction effect was not observed in subjects with Crohn's disease [see Clinical Pharmacology (12.3)].

7.3 Allergen Immunotherapy

Ustekinumab products have not been evaluated in patients who have undergone allergy immunotherapy. Ustekinumab products may decrease the protective effect of allergen immunotherapy (decrease tolerance) which may increase the risk of an allergic reaction to a dose of allergen immunotherapy. Therefore, caution should be exercised in patients receiving or who have received allergen immunotherapy, particularly for anaphylaxis.

8 USE IN SPECIFIC POPULATIONS

8.1 Pregnancy

Risk Summary

Available data from the Organization of Teratology Information Specialists (OTIS)/MotherToBaby Pregnancy Registry, published literature and pharmacovigilance in pregnant women have not identified a ustekinumab-associated risk of major birth defects, miscarriage or other adverse maternal or fetal outcomes (see Data). There are risks to the mother and the fetus associated with inflammatory bowel disease (IBD) in pregnancy. In animal reproductive and developmental toxicity studies, no adverse developmental effects were observed in offspring after administration of ustekinumab to pregnant monkeys at exposures greater than 100 times the maximum recommended human dose (MRHD).

All pregnancies have a background risk of birth defect, loss, or other adverse outcomes. In the U.S. general population, the estimated background risk of major birth defects and miscarriage of clinically recognized pregnancies is 2% to 4% and 15% to 20%, respectively.

Clinical Considerations

Disease-associated Maternal and Embryo/Fetal Risk

Published data suggest that the risk of adverse pregnancy outcomes in women with IBD is associated with increased disease activity. Adverse pregnancy outcomes include preterm delivery (before 37 weeks of gestation), low birth weight (less than 2500 g) infants, and small for gestational age at birth.

Fetal/Neonatal Adverse Reactions

Transport of endogenous IgG antibodies across the placenta increases as pregnancy progresses, and peaks during the third trimester. Therefore, ustekinumab products may be present in infants exposed in utero. The potential clinical impact of ustekinumab product exposure in infants exposed in utero should be considered.

Data

Human Data

An observational pregnancy registry conducted by (OTIS)/MotherToBaby in the U.S. and Canada (enrollment between 2013 and 2019) assessed the risk of major birth defects, pattern of major and minor anomalies in live-born infants, miscarriage, and adverse infant outcomes in women with ustekinumab exposure. In the registry study, there were 101 participants and 107 pregnancies with exposure to ustekinumab (88 prospective; 19 retrospective). Most participants had a primary indication of CD (65.4%) or psoriasis (30.8%). The pregnancy registry did not identify a ustekinumab-associated risk of major birth defects, pattern of major or minor anomalies, increased risk of miscarriage or adverse infant outcomes. Methodological limitations of the registry include small sample size, lack of an internal comparison group, a mix of prospective and retrospective reports, and unmeasured confounders. The conclusions from the pregnancy registry were consistent with the published literature and pharmacovigilance.

Animal Data

Ustekinumab was tested in two embryo-fetal development toxicity studies in cynomolgus monkeys. No teratogenic or other adverse developmental effects were observed in fetuses from pregnant monkeys that were administered ustekinumab subcutaneously twice weekly or intravenously weekly during the period of organogenesis. Serum concentrations of ustekinumab in pregnant monkeys were greater than 100 times the serum concentration in patients treated subcutaneously with 90 mg of ustekinumab weekly for 4 weeks.

In a combined embryo-fetal development and pre- and post-natal development toxicity study, pregnant cynomolgus monkeys were administered subcutaneous doses of ustekinumab twice weekly at exposures greater than 100 times the MRHD from the beginning of organogenesis to Day 33 after delivery. Neonatal deaths occurred in the offspring of one monkey administered ustekinumab at 22.5 mg/kg and one monkey dosed at 45 mg/kg. No ustekinumab-related effects on functional, morphological, or immunological development were observed in the neonates from birth through six months of age.

8.2 Lactation

Risk Summary

Limited data from published literature suggests that ustekinumab is present in human breast milk. There are no available data on the effects of ustekinumab products on milk production. The effects of local gastrointestinal exposure and limited systemic exposure in the breastfed infant to ustekinumab products are unknown. No adverse effects on the breastfed infant causally related to ustekinumab products have been identified in the published literature or postmarketing experience.

The developmental and health benefits of breastfeeding should be considered along with the mother's clinical need for PYZCHIVA and any potential adverse effects on the breastfed child from PYZCHIVA or from the underlying maternal condition.

8.4 Pediatric Use

Plaque Psoriasis

The safety and effectiveness of PYZCHIVA have been established for the treatment of moderate to severe plaque psoriasis in pediatric patients 6 years of age and older who are candidates for phototherapy or systemic therapy.

Use of PYZCHIVA in pediatric patients 12 to less than 17 years of age is supported by evidence from a multicenter, randomized, 60 week trial (Ps STUDY 3) of ustekinumab that included a 12 week, double-blind, placebo-controlled, parallel group portion, in 110 pediatric subjects 12 years of age and older [see Adverse Reactions (6.1), Clinical Studies (14.2)].

Use of PYZCHIVA in pediatric patients 6 to 11 years of age is supported by evidence from an open- label, single-arm, efficacy, safety and pharmacokinetics trial (Ps STUDY 4) of ustekinumab in 44 subjects [see Adverse Reactions (6.1), Clinical Pharmacology (12.3)].

The safety and effectiveness of PYZCHIVA have not been established in pediatric patients less than 6 years of age with plaque psoriasis.
Psoriatic Arthritis

The safety and effectiveness of PYZCHIVA have been established for treatment of psoriatic arthritis in pediatric patients 6 years of age and older.

Use of PYZCHIVA in these age groups is supported by evidence from adequate and well controlled trials of ustekinumab in adult subjects with psoriasis and PsA, pharmacokinetic data from adult subjects with psoriasis, adult subjects with PsA and pediatric subjects with psoriasis, and safety data of ustekinumab from two clinical trials in 44 pediatric subjects 6 to 11 years old with psoriasis and 110 pediatric subjects 12 years of age and older with psoriasis. The observed pre-dose (trough) concentrations are generally comparable between adult subjects with psoriasis, adult subjects with PsA and pediatric subjects with psoriasis, and the PK exposure is expected to be comparable between adult and pediatric subjects with PsA [see Adverse Reactions (6.1), Clinical Pharmacology (12.3), and Clinical Studies (14.1, 14.2, 14.3)].

The safety and effectiveness of PYZCHIVA have not been established in pediatric patients less than 6 years old with psoriatic arthritis.

Crohn's Disease and Ulcerative Colitis

The safety and effectiveness of PYZCHIVA have not been established in pediatric patients with Crohn's disease or ulcerative colitis.

8.5 Geriatric Use

Of the 6709 subjects exposed to ustekinumab, a total of 340 were 65 years of age or older (183 subjects with plaque psoriasis, 65 subjects with psoriatic arthritis, 58 subjects with Crohn's disease and 34 subjects with ulcerative colitis), and 40 subjects were 75 years of age or older. Clinical trials of ustekinumab did not include sufficient numbers of subjects 65 years of age and older to determine whether they respond differently from younger adult subjects.

10 OVERDOSAGE

Single doses up to 6 mg/kg intravenously have been administered in clinical trials without dose-limiting toxicity. In case of overdosage, monitor the patient for any signs or symptoms of adverse reactions or effects and institute appropriate symptomatic treatment immediately. Consider contacting the Poison Help line 1-800-222-1222 or a medical toxicologist for additional overdose management recommendations.

11 DESCRIPTION

Ustekinumab-ttwe, a human IgG1κ monoclonal antibody, is a human interleukin-12 and -23 antagonist. Using DNA recombinant technology, ustekinumab-ttwe is produced in a Chinese hamster ovary cell line. The manufacturing process contains steps for the clearance of viruses. Ustekinumab-ttwe is comprised of 1326 amino acids and has an estimated molecular mass that ranges from 148,079 to 149,690 Daltons.

PYZCHIVA (ustekinumab-ttwe) injection is a clear, colorless to light yellow, sterile and preservative-free solution with pH of 5.7– 6.3.

PYZCHIVA for Subcutaneous Use

Available as 45 mg of ustekinumab-ttwe in 0.5 mL and 90 mg of ustekinumab-ttwe in 1 mL, supplied as a sterile solution in a single-dose prefilled syringe with a 29 gauge fixed ½ inch needle and as 45 mg of ustekinumab-ttwe in 0.5 mL in a single-dose Type I glass vial with a coated stopper. The syringe is fitted with a passive needle guard and a needle cover.

Available as 45 mg of ustekinumab-ttwe in 0.5 mL and 90 mg of ustekinumab-ttwe in 1 mL, supplied as a sterile solution in a single-dose prefilled autoinjector.

Each 0.5 mL prefilled syringe, prefilled PYZCHIVA AUTOINJECTOR or vial delivers 45 mg ustekinumab-ttwe, histidine (0.095 mg), histidine hydrochloride monohydrate (0.405 mg), polysorbate 80 (0.02 mg), and sucrose (42.5 mg).

Each 1 mL prefilled syringe or prefilled PYZCHIVA AUTOINJECTOR delivers 90 mg ustekinumab-ttwe, histidine (0.19 mg), histidine hydrochloride monohydrate (0.81 mg), polysorbate 80 (0.04 mg), and sucrose (85 mg).

PYZCHIVA for Intravenous Infusion

Available as 130 mg of ustekinumab-ttwe in 26 mL, supplied as a single-dose Type I glass vial with a coated stopper.

Each 26 mL vial delivers 130 mg ustekinumab-ttwe, edetate disodium (0.52 mg), histidine (20 mg), histidine hydrochloride monohydrate (27 mg), methionine (10.4 mg), polysorbate 80 (10.4 mg) and sucrose (2,210 mg).

12 CLINICAL PHARMACOLOGY

12.1 Mechanism of Action

Ustekinumab products are human IgG1κ monoclonal antibodies that bind with specificity to the p40 protein subunit used by both the IL-12 and IL-23 cytokines. IL-12 and IL-23 are naturally occurring cytokines that are involved in inflammatory and immune responses, such as natural killer cell activation and CD4+ T-cell differentiation and activation. In in vitro models, ustekinumab products were shown to disrupt IL-12 and IL-23 mediated signaling and cytokine cascades by disrupting the interaction of these cytokines with a shared cell- surface receptor chain, IL-12Rβ1. The cytokines IL-12 and IL-23 have been implicated as important contributors to the chronic inflammation that is a hallmark of Crohn's disease and ulcerative colitis. In animal models of colitis, genetic absence or antibody blockade of the p40 subunit of IL-12 and IL-23, the target of ustekinumab products, was shown to be protective.

12.2 Pharmacodynamics

Plaque Psoriasis

In a small exploratory trial, a decrease was observed in the expression of mRNA of its molecular targets IL-12 and IL-23 in lesional skin biopsies measured at baseline and up to two weeks post-treatment in subjects with plaque psoriasis.

Ulcerative Colitis

In both trial UC-1 (induction) and trial UC-2 (maintenance), a positive relationship was observed between exposure and rates of clinical remission, clinical response, and endoscopic improvement. The response rate approached a plateau at the ustekinumab exposures associated with the recommended dosing regimen for maintenance treatment [see Clinical Studies (14.5)].

12.3 Pharmacokinetics

Absorption

In adult subjects with plaque psoriasis, the median time to reach the maximum serum concentration (Tmax) was 13.5 days and 7 days, respectively, after a single subcutaneous administration of 45 mg (N=22) and 90 mg (N=24) of ustekinumab. In healthy subjects (N=30), the median Tmax value (8.5 days) following a single subcutaneous administration of 90 mg of ustekinumab was comparable to that observed in subjects with plaque psoriasis.

Following multiple subcutaneous doses of ustekinumab in adult subjects with plaque psoriasis, steady-state serum concentrations of ustekinumab were achieved by Week 28. The mean (±SD) steady-state trough serum ustekinumab concentrations were 0.69 ± 0.69 mcg/mL for subjects less than or equal to 100 kg receiving a 45 mg dose and 0.74 ± 0.78 mcg/mL for subjects greater than 100 kg receiving a 90 mg dose. There was no apparent accumulation in serum ustekinumab concentration over time when given subcutaneously every 12 weeks.

Following the recommended intravenous induction dose, mean ±SD peak serum ustekinumab concentration was 125.2 ± 33.6 mcg/mL in subjects with Crohn's disease, and 129.1 ± 27.6 mcg/mL in subjects with ulcerative colitis. Starting at Week 8, the recommended subcutaneous maintenance dosing of 90 mg ustekinumab was administered every 8 weeks. Steady state ustekinumab concentration was achieved by the start of the second maintenance dose. There was no apparent accumulation in ustekinumab concentration over time when given subcutaneously every 8 weeks. Mean ± SD steady-state trough concentration was 2.5 ± 2.1 mcg/mL in subjects with Crohn's disease, and 3.3 ± 2.3 mcg/mL in subjects with ulcerative colitis for 90 mg ustekinumab administered every 8 weeks.

Distribution

Population pharmacokinetic analyses showed that the volume of distribution of ustekinumab in the central compartment was 2.7 L (95% CI: 2.69, 2.78) in subjects with Crohn's disease and 3.0 L (95% CI: 2.96, 3.07) in subjects with ulcerative colitis. The total volume of distribution at steady-state was 4.6 L in subjects with Crohn's disease and 4.4 L in subjects with ulcerative colitis.

Elimination

The mean (±SD) half-life ranged from 14.9 ± 4.6 to 45.6 ± 80.2 days across all trials in subjects with plaque psoriasis following subcutaneous administration. Population pharmacokinetic analyses showed that the clearance of ustekinumab was 0.19 L/day (95% CI: 0.185, 0.197) in subjects with Crohn's disease and 0.19 L/day (95% CI: 0.179, 0.192) in subjects with ulcerative colitis with an estimated median terminal half-life of approximately 19 days for both IBD (Crohn's disease and ulcerative colitis) populations.

These results indicate the pharmacokinetics of ustekinumab were similar between subjects with Crohn's disease and ulcerative colitis.

Metabolism

The metabolic pathway of ustekinumab products has not been characterized. As a human IgG1κ monoclonal antibody, ustekinumab products are expected to be degraded into small peptides and amino acids via catabolic pathways in the same manner as endogenous IgG.

Specific Populations

Weight

When given the same dose, subjects with plaque psoriasis or psoriatic arthritis weighing more than 100 kg had lower median serum ustekinumab concentrations compared with those subjects weighing 100 kg or less. The median trough serum concentrations of ustekinumab in subjects of higher weight (greater than 100 kg) in the 90 mg group were comparable to those in subjects of lower weight (100 kg or less) in the 45 mg group.

Age: Geriatric Population

A population pharmacokinetic analysis (N=106/1937 subjects with plaque psoriasis greater than or equal to 65 years old) was performed to evaluate the effect of age on the pharmacokinetics of ustekinumab. There were no apparent changes in pharmacokinetic parameters (clearance and volume of distribution) in subjects older than 65 years old.

Age: Pediatric Population

Following multiple recommended doses of ustekinumab in pediatric subjects 6 years of age and older with plaque psoriasis, steady-state serum concentrations of ustekinumab were achieved by Week 28. At Week 28, the mean ±SD steady-state trough serum ustekinumab concentrations were 0.36 ± 0.26 mcg/mL and 0.54 ± 0.43 mcg/mL, respectively, in pediatric subjects 6 to 11 years of age and pediatric subjects 12 years of age and older.

Overall, the observed steady-state ustekinumab trough concentrations in pediatric subjects with plaque psoriasis were within the range of those observed for adult subjects with plaque psoriasis and adult subjects with PsA after administration of ustekinumab.

Drug Interaction Studies

The effects of IL-12 or IL-23 on the regulation of CYP450 enzymes were evaluated in an in vitro study using human hepatocytes, which showed that IL-12 and/or IL-23 at levels of 10 ng/mL did not alter human CYP450 enzyme activities (CYP1A2, 2B6, 2C9, 2C19, 2D6, or 3A4).

No clinically significant changes in exposure of caffeine (CYP1A2 substrate), warfarin (CYP2C9 substrate), omeprazole (CYP2C19 substrate), dextromethorphan (CYP2D6 substrate), or midazolam (CYP3A substrate) were observed when used concomitantly with ustekinumab at the approved recommended dosage in subjects with Crohn's disease [see Drug Interactions (7.2)].

Population pharmacokinetic analyses indicated that the clearance of ustekinumab was not impacted by concomitant MTX, NSAIDs, and oral corticosteroids, or prior exposure to a TNF blocker in subjects with psoriatic arthritis.

In subjects with Crohn's disease and ulcerative colitis, population pharmacokinetic analyses did not indicate changes in ustekinumab clearance with concomitant use of corticosteroids or immunomodulators (AZA, 6-MP, or MTX); and serum ustekinumab concentrations were not impacted by concomitant use of these medications.

13 NONCLINICAL TOXICOLOGY

13.1 Carcinogenesis, Mutagenesis, Impairment of Fertility

Animal studies have not been conducted to evaluate the carcinogenic or mutagenic potential of ustekinumab products. Published literature showed that administration of murine IL-12 caused an anti-tumor effect in mice that contained transplanted tumors and IL-12/IL- 23p40 knockout mice or mice treated with anti-IL-12/IL-23p40 antibody had decreased host defense to tumors. Mice genetically manipulated to be deficient in both IL-12 and IL- 23 or IL-12 alone developed UV-induced skin cancers earlier and more frequently compared to wild-type mice. The relevance of these experimental findings in mouse models for malignancy risk in humans is unknown.

No effects on fertility were observed in male cynomolgus monkeys that were administered ustekinumab at subcutaneous doses up to 45 mg/kg twice weekly (45 times the MRHD on a mg/kg basis) prior to and during the mating period. However, fertility and pregnancy outcomes were not evaluated in mated females.

No effects on fertility were observed in female mice that were administered an analogous IL-12/IL-23p40 antibody by subcutaneous administration at doses up to 50 mg/kg, twice weekly, prior to and during early pregnancy.

13.2 Animal Toxicology and/or Pharmacology

In a 26-week toxicology study, one out of 10 monkeys subcutaneously administered 45 mg/kg ustekinumab twice weekly for 26 weeks had a bacterial infection.

14 CLINICAL STUDIES

14.1 Adult Subjects with Plaque Psoriasis

Two multicenter, randomized, double-blind, placebo-controlled trials (Ps STUDY 1 and Ps STUDY 2) enrolled a total of 1996 subjects 18 years of age and older with plaque psoriasis who had a minimum body surface area involvement of 10%, and Psoriasis Area and Severity Index (PASI) score ≥12, and who were candidates for phototherapy or systemic therapy. Subjects with guttate, erythrodermic, or pustular psoriasis were excluded from the trials.

Ps STUDY 1 enrolled 766 subjects and Ps STUDY 2 enrolled 1230 subjects. The trials had the same design through Week 28. In both trials, subjects were randomized in equal proportion to placebo, 45 mg or 90 mg of ustekinumab. Subjects randomized to ustekinumab received 45 mg or 90 mg doses, regardless of weight, at Weeks 0, 4, and 16. Subjects randomized to receive placebo at Weeks 0 and 4 crossed over to receive ustekinumab (either 45 mg or 90 mg) at Weeks 12 and 16.

In both trials, subjects in all treatment groups had a median baseline PASI score ranging from approximately 17 to 18. Baseline PGA score was marked or severe in 44% of subjects in Ps STUDY 1 and 40% of subjects in Ps STUDY 2. Approximately two-thirds of all subjects had received prior phototherapy, 69% had received either prior conventional systemic or biologic therapy for the treatment of psoriasis, with 56% receiving prior conventional systemic therapy and 43% receiving prior biologic therapy. A total of 28% of subjects had a history of psoriatic arthritis.

In both trials, the endpoints were the proportion of subjects who achieved at least a 75% reduction in PASI score (PASI 75) from baseline to Week 12 and treatment success (cleared or minimal) on the Physician's Global Assessment (PGA). The PGA is a 6- category scale ranging from 0 (cleared) to 5 (severe) that indicates the physician's overall assessment of psoriasis focusing on plaque thickness/induration, erythema, and scaling.

Clinical Response

The results of Ps STUDY 1 and Ps STUDY 2 are presented in Table 8 below.

Table 8: Clinical Outcomes at Week 12 in Adult Subjects with Plaque Psoriasis in Ps STUDY 1 and Ps STUDY 2
 | Ps STUDY 1 Ustekinumab |  |  | Ps STUDY 2 Ustekinumab
 | Placebo | 45 mg | 90 mg | Placebo | 45 mg | 90 mg
Subjects randomized | 255 | 255 | 256 | 410 | 409 | 411
PASI 75 response | 8 (3%) | 171 (67%) | 170 (66%) | 15 (4%) | 273 (67%) | 311 (76%)
PGA of Cleared or Minimal | 10 (4%) | 151 (59%) | 156 (61%) | 18 (4%) | 277 (68%) | 300 (73%)

Examination of age, gender, and race subgroups did not identify differences in response to ustekinumab among these subgroups.

In subjects who weighed 100 kg or less, response rates were comparable with both the 45 mg and 90 mg doses; however, in subjects who weighed greater than 100 kg, higher response rates were seen with 90 mg dosing compared with 45 mg dosing (Table 9 below).

Table 9: Clinical Outcomes by Weight at Week 12 in Adult Subjects with Plaque Psoriasis in Ps STUDY 1 and Ps STUDY 2
 | Ps STUDY 1 Ustekinumab |  |  | Ps STUDY 2 Ustekinumab
 | Placebo | 45 mg | 90 mg | Placebo | 45 mg | 90 mg
Subjects randomized | 255 | 255 | 256 | 410 | 409 | 411
PASI 75 response*
≤100 kg | 4% | 74% | 65% | 4% | 73% | 78%
 | 6/166 | 124/168 | 107/164 | 12/290 | 218/297 | 225/289
>100 kg | 2% | 54% | 68% | 3% | 49% | 71%
 | 2/89 | 47/87 | 63/92 | 3/120 | 55/112 | 86/121
PGA of Cleared or Minimal *
≤100 kg | 4% | 64% | 63% | 5% | 74% | 75%
 | 7/166 | 108/168 | 103/164 | 14/290 | 220/297 | 216/289
>100 kg | 3% | 49% | 58% | 3% | 51% | 69%
 | 3/89 | 43/87 | 53/92 | 4/120 | 57/112 | 84/121

* Subjects were dosed with trial medication at Weeks 0 and 4.

Subjects in Ps STUDY 1 who were PASI 75 responders at both Weeks 28 and 40 were re-randomized at Week 40 to either continued dosing of ustekinumab (ustekinumab at Week 40) or to withdrawal of therapy (placebo at Week 40). At Week 52, 89% (144/162) of subjects re-randomized to ustekinumab treatment were PASI 75 responders compared with 63% (100/159) of subjects re-randomized to placebo (treatment withdrawal after Week 28 dose). The median time to loss of PASI 75 response among the subjects randomized to treatment withdrawal was 16 weeks.

14.2 Pediatric Subjects with Plaque Psoriasis

A multicenter, randomized, double blind, placebo-controlled trial (Ps STUDY 3) enrolled 110 pediatric subjects 12 years of age and older with a minimum BSA involvement of 10%, a PASI score greater than or equal to 12, and a PGA score greater than or equal to 3, who were candidates for phototherapy or systemic therapy and whose disease was inadequately controlled by topical therapy.

Subjects were randomized to receive placebo (n = 37), the recommended dose of ustekinumab (n = 36), or one-half the recommended dose of ustekinumab (n = 37) by subcutaneous injection at Weeks 0 and 4 followed by dosing every 12 weeks (q12w). The recommended dose of ustekinumab was 0.75 mg/kg for subjects weighing less than 60 kg, 45 mg for subjects weighing 60 kg to 100 kg, and 90 mg for subjects weighing greater than 100 kg. At Week 12, subjects who received placebo were crossed over to receive ustekinumab at the recommended dose or one-half the recommended dose.

Of the pediatric subjects, approximately 63% had prior exposure to phototherapy or conventional systemic therapy and approximately 11% had prior exposure to biologics.

The endpoints were the proportion of subjects who achieved a PGA score of cleared (0) or minimal (1), PASI 75, and PASI 90 at Week 12. Subjects were followed for up to 60 weeks following first administration of trial agent.

Clinical Response

The efficacy results at Week 12 for Ps STUDY 3 are presented in Table 10.

Table 10: Efficacy Results at Week 12 in Pediatric Subjects 12 Years of Age and Older with Plaque Psoriasis in Ps STUDY 3
 | Ps STUDY 3
 | Placebo n (%) | Ustekinumab* n (%)
N | 37 | 36
PGA
PGA of cleared (0) or minimal (1) | 2 (5.4%) | 25 (69.4%)
PASI
PASI 75 responders | 4 (10.8%) | 29 (80.6%)
PASI 90 responders | 2 (5.4%) | 22 (61.1%)

* Using the weight-based dosage regimen specified in Table 1 and Table 2.

14.3 Psoriatic Arthritis

The safety and efficacy of ustekinumab was assessed in 927 subjects (PsA STUDY 1, n=615; PsA STUDY 2, n=312), in two randomized, double-blind, placebo-controlled trials in adult subjects 18 years of age and older with active PsA (≥5 swollen joints and ≥5 tender joints) despite nonsteroidal anti-inflammatory (NSAID) or disease modifying antirheumatic (DMARD) therapy. Subjects in these trials had a diagnosis of PsA for at least 6 months. Subjects with each subtype of PsA were enrolled, including polyarticular arthritis with the absence of rheumatoid nodules (39%), spondylitis with peripheral arthritis (28%), asymmetric peripheral arthritis (21%), distal interphalangeal involvement (12%) and arthritis mutilans (0.5%). Over 70% and 40% of the subjects, respectively, had enthesitis and dactylitis at baseline.

Subjects were randomized to receive treatment with ustekinumab 45 mg, 90 mg, or placebo subcutaneously at Weeks 0 and 4 followed by every 12 weeks (q12w) dosing. Approximately 50% of subjects continued on stable doses of MTX (≤25 mg/week). The primary endpoint was the percentage of subjects achieving ACR 20 response at Week 24.

In PsA STUDY 1 and PsA STUDY 2, 80% and 86% of the subjects, respectively, had been previously treated with DMARDs. In PsA STUDY 1, previous treatment with anti-tumor necrosis factor (TNF)-α agent was not allowed. In PsA STUDY 2, 58% (n=180) of the subjects had been previously treated with TNF blocker, of whom over 70% had discontinued their TNF blocker treatment for lack of efficacy or intolerance at any time.

Clinical Response

In both trials, a greater proportion of subjects achieved ACR 20, ACR 50 and PASI 75 response in the ustekinumab 45 mg and 90 mg groups compared to placebo at Week 24 (see Table 11). ACR 70 responses were also higher in the ustekinumab 45 mg and 90 mg groups, although the difference was only numerical (p=NS) in STUDY 2. Responses were consistent in subjects treated with ustekinumab alone or in combination with methotrexate. Responses were similar in subjects regardless of prior TNFα exposure.

Table 11: ACR 20, ACR 50, ACR 70 and PASI 75 responses in PsA STUDY 1 and PsA STUDY 2 at Week 24
 | PsA STUDY 1 Ustekinumab |  |  | PsA STUDY 2 Ustekinumab
 | Placebo | 45 mg | 90 mg | Placebo | 45 mg | 90 mg
Number of subjects Randomized | 206 | 205 | 204 | 104 | 103 | 105
ACR 20 response, N (%) | 47 (23%) | 87 (42%) | 101 (50%) | 21 (20%) | 45 (44%) | 46 (44%)
ACR 50 response, N (%) | 18 (9%) | 51 (25%) | 57 (28%) | 7 (7%) | 18 (17%) | 24 (23%)
ACR 70 response, N (%) | 5 (2%) | 25 (12%) | 29 (14%) | 3 (3%) | 7 (7%) | 9 (9%)
Number of subjects with ≥ 3% BSA* | 146 | 145 | 149 | 80 | 80 | 81
PASI 75 response, N (%) | 16 (11%) | 83 (57%) | 93 (62%) | 4 (5%) | 41 (51%) | 45 (56%)

*Number of subjects with ≥ 3% BSA psoriasis skin involvement at baseline

The percent of subjects achieving ACR 20 responses by visit is shown in Figure 1.

Figure 1: Percent of subjects achieving ACR 20 response through Week 24

The results of the components of the ACR response criteria are shown in Table 12.

Table 12: Mean change from baseline in ACR components at Week 24
 | PsA STUDY 1
 | Placebo (N = 206) | Ustekinumab
 | Placebo (N = 206) | 45 mg (N = 205) | 90 mg (N = 204)
Number of swollen jointsa
Baseline | 15 | 12 | 13
Mean Change at Week 24 | -3 | -5 | -6
Number of tender jointsb
Baseline | 25 | 22 | 23
Mean Change at Week 24 | -4 | -8 | -9
Subject's assessment of painc
Baseline | 6.1 | 6.2 | 6.6
Mean Change at Week 24 | -0.5 | -2.0 | -2.6
Subject global assessmentc
Baseline | 6.1 | 6.3 | 6.4
Mean Change at Week 24 | -0.5 | -2.0 | -2.5
Physician global assessmentc
Baseline | 5.8 | 5.7 | 6.1
Mean Change at Week 24 | -1.4 | -2.6 | -3.1
Disability index (HAQ)d
Baseline | 1.2 | 1.2 | 1.2
Mean Change at Week 24 | -0.1 | -0.3 | -0.4
CRP (mg/dL)e
Baseline | 1.6 | 1.7 | 1.8
Mean Change at Week 24 | 0.01 | -0.5 | -0.8

a Number of swollen joints counted (0–66)
b Number of tender joints counted (0–68)
c Visual analogue scale; 0= best, 10=worst.
d Disability Index of the Health Assessment Questionnaire; 0 = best, 3 = worst, measures the patient's ability to perform the following: dress/groom, arise, eat, walk, reach, grip, maintain hygiene, and maintain daily activity.
e CRP: (Normal Range 0.0–1.0 mg/dL)

An improvement in enthesitis and dactylitis scores was observed in each ustekinumab group compared with placebo at Week 24.

Physical Function

Ustekinumab-treated subjects showed improvement in physical function compared to subjects receiving placebo as assessed by HAQ-DI at Week 24. In both trials, the proportion of HAQ-DI responders (≥0.3 improvement in HAQ-DI score) was greater in the ustekinumab 45 mg and 90 mg groups compared to placebo at Week 24.

14.4 Crohn's Disease

Ustekinumab was evaluated in three randomized, double-blind, placebo-controlled clinical trials in adult subjects with moderately to severely active Crohn's disease (Crohn's Disease Activity Index [CDAI] score of 220 to 450). There were two 8-week intravenous induction trials (CD-1 and CD-2) followed by a 44-week subcutaneous randomized withdrawal maintenance trial (CD-3) representing 52 weeks of therapy. Subjects in CD- 1 had failed or were intolerant to treatment with one or more TNF blockers, while subjects in CD-2 had failed or were intolerant to treatment with immunomodulators or corticosteroids, but never failed treatment with a TNF blocker.

Trials CD-1 and CD-2

In trials CD-1 and CD-2, 1409 subjects were randomized, of whom 1368 (CD-1, n=741; CD-2, n=627) were included in the final efficacy analysis. Induction of clinical response (defined as a reduction in CDAI score of greater than or equal to 100 points or CDAI score of less than 150) at Week 6 and clinical remission (defined as a CDAI score of less than 150) at Week 8 were evaluated. In both trials, subjects were randomized to receive a single intravenous administration of ustekinumab at either approximately 6 mg/kg, placebo (see Table 4), or 130 mg (a lower dose than recommended).

In trial CD-1, subjects had failed or were intolerant to prior treatment with a TNF blocker: 29% subjects had an inadequate initial response (primary non-responders), 69% responded but subsequently lost response (secondary non-responders) and 36% were intolerant to a TNF blocker. Of these subjects, 48% failed or were intolerant to one TNF blocker and 52% had failed 2 or 3 prior TNF blockers. At baseline and throughout the trial, approximately 46% of the subjects were receiving corticosteroids and 31% of the subjects were receiving immunomodulators (AZA, 6-MP, MTX). The median baseline CDAI score was 319 in the ustekinumab approximately 6 mg/kg group and 313 in the placebo group.

In trial CD-2, subjects had failed or were intolerant to prior treatment with corticosteroids (81% of subjects), at least one immunomodulator (6-MP, AZA, MTX; 68% of subjects), or both (49% of subjects). Additionally, 69% never received a TNF blocker and 31% previously received but had not failed a TNF blocker. At baseline, and throughout the trial, approximately 39% of the subjects were receiving corticosteroids and 35% of the subjects were receiving immunomodulators (AZA, 6-MP, MTX). The median baseline CDAI score was 286 in the ustekinumab and 290 in the placebo group.

In these induction trials, a greater proportion of subjects treated with ustekinumab (at the recommended dose of approximately 6 mg/kg dose) achieved clinical response at Week 6 and clinical remission at Week 8 compared to placebo (see Table 13 for clinical response and remission rates). Clinical response and remission were significant as early as Week 3 in ustekinumab-treated subjects and continued to improve through Week 8.

Table 13: Induction of Clinical Response and Remission in CD-1* and CD-2**
 | CD-1 n = 741 |  |  | CD-2 n = 627
 | Placebo N = 247 | Ustekinumab† N = 249 | Treatment difference and 95% Cl | Placebo N = 209 | Ustekinumab† N = 209 | Treatment difference and 95% Cl
Clinical Response (100 point), Week 6 | 53 (21%) | 84 (34%)a | 12% (4%, 20%) | 60 (29%) | 116 (56%)b | 27% (18%, 36%)
Clinical Remission, Week 8 | 18 (7%) | 52 (21%)b | 14% (8%, 20%) | 41 (20%) | 84 (40%)b | 21% (12%, 29%)
Clinical Response (100 point), Week 8 | 50 (20%) | 94 (38%)b | 18% (10%, 25%) | 67 (32%) | 121 (58%)b | 26% (17%, 35%)
70 Point Response, Week 6 | 75 (30%) | 109 (44%)a | 13% (5%, 22%) | 81 (39%) | 135 (65%)b | 26% (17%, 35%)
70 Point Response, Week 3 | 67 (27%) | 101 (41%)a | 13% (5%, 22%) | 66 (32%) | 106 (51%)b | 19% (10%, 28%)

Clinical remission is defined as CDAI score < 150; Clinical response is defined as reduction in CDAI score by at least 100 points or being in clinical remission: 70 point response is defined as reduction in CDAI score by at least 70 points
* Patient population consisted of subjects who failed or were intolerant to TNF blocker therapy
** Patient population consisted of subjects who failed or were intolerant to corticosteroids or immunomodulators (e.g., 6-MP, AZA, MTX) and previously received but not failed a TNF blocker or were never treated with a TNF blocker.
† Infusion dose of ustekinumab using the weight-based dosage regimen specified in Table 4.
a 0.001 ≤ p < 0.01
b p < 0.001

Trial CD-3

The maintenance trial (CD-3), evaluated 388 subjects who achieved clinical response (≥ 100 point reduction in CDAI score) at Week 8 with either induction dose of ustekinumab in trials CD-1 or CD-2. Subjects were randomized to receive a subcutaneous maintenance regimen of either 90 mg ustekinumab every 8 weeks or placebo for 44 weeks (see Table 14).

Table 14: Clinical Response and Remission in CD-3 (Week 44; 52 weeks from initiation of the induction dose)
 | Placebo* N = 131** | 90 mg ustekinumab every 8 weeks N = 128** | Treatment difference and 95% CI
Clinical Remission | 47 (36%) | 68 (53%)† | 17% (5%, 29%)
Clinical Response | 58 (44%) | 76 (59%)a | 15% (3%, 27%)
Clinical Remission in subjects in remission at the start of maintenance therapyb | 36/79 (46%) | 52/78 (67%)† | 21% (6%, 36%)

Clinical remission is defined as CDAI score < 150; Clinical response is defined as reduction in CDAI of at least 100 points or being in clinical remission
* The placebo group consisted of subjects who were in response to ustekinumab and were randomized to receive placebo at the start of maintenance therapy.
** Subjects who achieved clinical response to ustekinumab at the end of the induction trial.
† p < 0.01
a 0.01≤ p < 0.05
b Subjects in remission at the end of maintenance therapy who were in remission at the start of maintenance therapy. This does not account for any other time point during maintenance therapy.

At Week 44, 47% of subjects who received ustekinumab were corticosteroid-free and in clinical remission, compared to 30% of subjects in the placebo group.

At Week 0 of trial CD-3, 34/56 (61%) ustekinumab-treated subjects who previously failed or were intolerant to TNF blocker therapies were in clinical remission and 23/56 (41%) of these subjects were in clinical remission at Week 44. In the placebo arm, 27/61 (44%) subjects were in clinical remission at Week 0 while 16/61 (26%) of these subjects were in remission at Week 44.

At Week 0 of trial CD-3, 46/72 (64%) ustekinumab-treated subjects who had previously failed immunomodulator therapy or corticosteroids (but not TNF blockers) were in clinical remission and 45/72 (63%) of these subjects were in clinical remission at Week 44. In the placebo arm, 50/70 (71%) of these subjects were in clinical remission at Week 0 while 31/70 (44%) were in remission at Week 44. In the subset of these subjects who were also naïve to TNF blockers, 34/52 (65%) of ustekinumab-treated subjects were in clinical remission at Week 44 as compared to 25/51 (49%) in the placebo arm.

Subjects who were not in clinical response 8 weeks after ustekinumab induction were not included in the primary efficacy analyses for trial CD-3; however, these subjects were eligible to receive a 90 mg subcutaneous injection of ustekinumab upon entry into trial CD-3. Of these subjects, 102/219 (47%) achieved clinical response eight weeks later and were followed for the duration of the trial.

14.5 Ulcerative Colitis

Ustekinumab was evaluated in two randomized, double-blind, placebo-controlled clinical trials [UC-1 and UC-2 (NCT02407236)] in adult subjects with moderately to severely active ulcerative colitis who had an inadequate response to or failed to tolerate a biologic (i.e., TNF blocker and/or vedolizumab), corticosteroids, and/or 6-MP or AZA therapy. The 8-week intravenous induction trial (UC-1) was followed by the 44-week subcutaneous randomized withdrawal maintenance trial (UC-2) for a total of 52 weeks of therapy.

Disease assessment was based on the Mayo score, which ranged from 0 to 12 and has four subscores that were each scored from 0 (normal) to 3 (most severe): stool frequency, rectal bleeding, findings on centrally-reviewed endoscopy, and physician global assessment. Moderately to severely active ulcerative colitis was defined at baseline (Week 0) as Mayo score of 6 to 12, including a Mayo endoscopy subscore ≥2. An endoscopy score of 2 was defined by marked erythema, absent vascular pattern, friability, erosions; and a score of 3 was defined by spontaneous bleeding, ulceration. At baseline, subjects had a median Mayo score of 9, with 84% of subjects having moderate disease (Mayo score 6–10) and 15% having severe disease (Mayo score 11–12).

Subjects in these trials may have received other concomitant therapies including aminosalicylates, immunomodulatory agents (AZA, 6-MP, or MTX), and oral corticosteroids (prednisone).

Trial UC-1

In UC-1, 961 subjects were randomized at Week 0 to a single intravenous administration of ustekinumab of approximately 6 mg/kg, 130 mg (a lower dose than recommended), or placebo. Subjects enrolled in UC-1 had to have failed therapy with corticosteroids, immunomodulators or at least one biologic. A total of 51% had failed at least one biologic and 17% had failed both a TNF blocker and an integrin receptor blocker. Of the total population, 46% had failed corticosteroids or immunomodulators but were biologic-naïve and an additional 3% had previously received but had not failed a biologic. At induction baseline and throughout the trial, approximately 52% subjects were receiving oral corticosteroids, 28% subjects were receiving immunomodulators (AZA, 6-MP, or MTX) and 69% subjects were receiving aminosalicylates.

The primary endpoint was clinical remission at Week 8. Clinical remission with a definition of: Mayo stool frequency subscore of 0 or 1, Mayo rectal bleeding subscore of 0 (no rectal bleeding), and Mayo endoscopy subscore of 0 or 1 (Mayo endoscopy subscore of 0 defined as normal or inactive disease and Mayo subscore of 1 defined as presence of erythema, decreased vascular pattern and no friability) is provided in Table 15.

The secondary endpoints were clinical response, endoscopic improvement, and histologic-endoscopic mucosal improvement. Clinical response with a definition of (≥ 2 points and ≥ 30% decrease in modified Mayo score, defined as 3-component Mayo score without the Physician's Global Assessment, with either a decrease from baseline in the rectal bleeding subscore ≥1 or a rectal bleeding subscore of 0 or 1), endoscopic improvement with a definition of Mayo endoscopy subscore of 0 or 1, and histologic- endoscopic mucosal improvement with a definition of combined endoscopic improvement and histologic improvement of the colon tissue [neutrophil infiltration in <5% of crypts, no crypt destruction, and no erosions, ulcerations, or granulation tissue]) are provided in Table 15.

In UC-1, a significantly greater proportion of subjects treated with ustekinumab (at the recommended dose of approximately 6 mg/kg dose) were in clinical remission and response and achieved endoscopic improvement and histologic-endoscopic mucosal improvement compared to placebo (see Table 15).

Table 15: Proportion of Subjects Meeting Efficacy Endpoints at Week 8 in UC-1
Endpoint | Placebo N = 319 |  | Ustekinumab† N = 322 |  | Treatment difference and; 97.5% CIa
Endpoint | N | % | N | % | Treatment difference and; 97.5% CIa
Clinical Remission* | 22 | 7% | 62 | 19% | 12% (7%, 18%)b
Bio-naïve⸸ | 14/151 | 9% | 36/147 | 24%
Prior biologic failure | 7/161 | 4% | 24/166 | 14%
Endoscopic Improvement§ | 40 | 13% | 80 | 25% | 12% (6%, 19%)b
Bio-naïve⸸ | 28/151 | 19% | 43/147 | 29%
Prior biologic failure | 11/161 | 7% | 34/166 | 20%
Clinical Response¶ | 99 | 31% | 186 | 58% | 27% (18%, 35%)b
Bio-naïve⸸ | 55/151 | 36% | 94/147 | 64%
Prior biologic failure | 42/161 | 26% | 86/166 | 52%
Histologic-Endoscopic Mucosal Improvement‡ | 26 | 8% | 54 | 17% | 9% (3%, 14%)b
Bio-naïve⸸ | 19/151 | 13% | 30/147 | 20%
Prior biologic failure | 6/161 | 4% | 21/166 | 13%

† Infusion dose of ustekinumab using the weight-based dosage regimen specified in Table 4.
⸸ An additional 7 subjects on placebo and 9 subjects on ustekinumab (6 mg/kg) had been exposed to, but had not failed, biologics.
* Clinical remission was defined as Mayo stool frequency subscore of 0 or 1, Mayo rectal bleeding subscore of 0, and Mayo endoscopy subscore of 0 or 1 (modified so that 1 does not include friability).
§ Endoscopic improvement was defined as Mayo endoscopy subscore of 0 or 1 (modified so that 1 does not include friability).
¶ Clinical response was defined as a decrease from baseline in the modified Mayo score by ≥30% and ≥2 points, with either a decrease from baseline in the rectal bleeding subscore ≥1 or a rectal bleeding subscore of 0 or 1.
‡ Histologic-endoscopic mucosal improvement was defined as combined endoscopic improvement (Mayo endoscopy subscore of 0 or 1) and histologic improvement of the colon tissue (neutrophil infiltration in <5% of crypts, no crypt destruction, and no erosions, ulcerations, or granulation tissue).
a Adjusted treatment difference (97.5% CI)
b p < 0.001

The relationship of histologic-endoscopic mucosal improvement, as defined in UC-1, at Week 8 to disease progression and long-term outcomes was not evaluated during UC-1.

Rectal Bleeding and Stool Frequency Subscores

Decreases in rectal bleeding and stool frequency subscores were observed as early as Week 2 in ustekinumab-treated subjects.

Trial UC-2

The maintenance trial (UC-2) evaluated 523 subjects who achieved clinical response 8 weeks following the intravenous administration of either induction dose of ustekinumab in UC-1. These subjects were randomized to receive a subcutaneous maintenance regimen of either 90 mg ustekinumab every 8 weeks, or every 12 weeks (a lower dose than recommended), or placebo for 44 weeks.

The primary endpoint was the proportion of subjects in clinical remission at Week 44. The secondary endpoints included the proportion of subjects maintaining clinical response at Week 44, the proportion of subjects with endoscopic improvement at Week 44, the proportion of subjects with corticosteroid-free clinical remission at Week 44, and the proportion of subjects maintaining clinical remission at Week 44 among subjects who achieved clinical remission 8 weeks after induction.

Results of the primary and secondary endpoints at Week 44 in subjects treated with ustekinumab at the recommended dosage (90 mg every 8 weeks) compared to the placebo are shown in Table 16.

Table 16: Efficacy Endpoints of Maintenance at Week 44 in UC-2 (52 Weeks from Initiation of the Induction Dose)
Endpoint | Placebo* N = 175† |  | 90 mg ustekinumab every 8 weeks N = 176 |  | Treatment difference and 95% CI
 | N | % | N | % | Treatment difference and 95% CI
Clinical Remission** | 46 | 26% | 79 | 45% | 19% (9%, 28%) a
Bio-naïve⸸ | 30/84 | 36% | 39/79 | 49%
Prior biologic failure | 16/88 | 18% | 37/91 | 41%
Maintenance of Clinical Response at Week 44† | 84 | 48% | 130 | 74% | 26% (16%, 36%) a
Bio-naïve⸸ | 49/84 | 58% | 62/79 | 78%
Prior biologic failure | 35/88 | 40% | 64/91 | 70%
Endoscopic Improvement§ | 47 | 27% | 83 | 47% | 20% (11%, 30%) a
Bio-naïve⸸ | 29/84 | 35% | 42/79 | 53%
Prior biologic failure | 18/88 | 20% | 38/91 | 42%
Corticosteroid-free Clinical Remission‡ | 45 | 26% | 76 | 43% | 17% (8%, 27%) a
Bio-naïve⸸ | 30/84 | 36% | 38/79 | 48%
Prior biologic failure | 15/88 | 17% | 35/91 | 38%
Maintenance of Clinical Remission at Week 44 in subjects who achieved clinical remission 8 weeks after induction | 18/50 | 36% | 27/41 | 66% | 31% (12%, 50%) b
Bio-naïve⸸ | 12/27 | 44% | 14/20 | 70%
Prior biologic failure | 6/23 | 26% | 12/18 | 67%

⸸ An additional 3 subjects on placebo and 6 subjects on ustekinumab had been exposed to, but had not failed, biologics.
* The placebo group consisted of subjects who were in response to ustekinumab and were randomized to receive placebo at the start of maintenance therapy.
** Clinical remission was defined as Mayo stool frequency subscore of 0 or 1, Mayo rectal bleeding subscore of 0, and Mayo endoscopy subscore of 0 or 1 (modified so that 1 does not include friability).
† Clinical response was defined as a decrease from baseline in the modified Mayo score by ≥30% and ≥2 points, with either a decrease from baseline in the rectal bleeding subscore ≥1 or a rectal bleeding subscore of 0 or 1.
§ Endoscopic improvement was defined as Mayo endoscopy subscore of 0 or 1 (modified so that 1 does not include friability).
‡ Corticosteroid-free clinical remission was defined as subjects in clinical remission and not receiving corticosteroids at Week 44.
a p =<0.001
b p=0.004

Other Endpoints

Week 16 Responders to Ustekinumab Induction

Subjects who were not in clinical response 8 weeks after induction with ustekinumab in UC- 1 were not included in the primary efficacy analyses for trial UC-2; however, these subjects were eligible to receive a 90 mg subcutaneous injection of ustekinumab at Week 8. Of these subjects, 55/101 (54%) achieved clinical response eight weeks later (Week 16) and received ustekinumab 90 mg subcutaneously every 8 weeks during the UC-2 trial. At Week 44, there were 97/157 (62%) subjects who maintained clinical response and there were 51/157 (32%) who achieved clinical remission.

Histologic-Endoscopic Mucosal Improvement at Week 44

The proportion of subjects achieving histologic-endoscopic mucosal improvement during maintenance treatment in UC-2 was 75/172 (44%) among subjects on ustekinumab and 40/172 (23%) in subjects on placebo at Week 44. The relationship of histologic-endoscopic mucosal improvement, as defined in UC-2, at Week 44 to progression of disease or long-term outcomes was not evaluated in UC-2.

Endoscopic Normalization

Normalization of endoscopic appearance of the mucosa was defined as a Mayo endoscopic subscore of 0. At Week 8 in UC-1, endoscopic normalization was achieved in 25/322 (8%) of subjects treated with ustekinumab and 12/319 (4%) of subjects in the placebo group. At Week 44 of UC-2, endoscopic normalization was achieved in 51/176 (29%) of subjects treated with ustekinumab and in 32/175 (18%) of subjects in placebo group.

15 REFERENCES

1 Surveillance, Epidemiology, and End Results (SEER) Program (www.seer.cancer.gov) SEER*Stat Database: Incidence - SEER 6.6.2 Regs Research Data, Nov 2009 Sub (1973–2007) - Linked To County Attributes - Total U.S., 1969– 2007 Counties, National Cancer Institute, DCCPS, Surveillance Research Program, Surveillance Systems Branch, released April 2010, based on the November 2009 submission.

16 HOW SUPPLIED/STORAGE AND HANDLING

PYZCHIVA (ustekinumab-ttwe) injection is a clear, colorless to light yellow, sterile and preservative-free solution. It is supplied as individually packaged, single-dose prefilled syringe, single-dose prefilled PYZCHIVA AUTOINJECTOR or single-dose vial.

For Subcutaneous Use

Prefilled Syringes

- 45 mg/0.5 mL (NDC 83457-651-01)
- 90 mg/mL (NDC 83457-652-01)

Each prefilled syringe is equipped with a 29 gauge fixed ½ inch needle, a needle safety guard, and a needle cover that is not made with natural rubber latex.

Prefilled Autoinjector (PYZCHIVA AUTOINJECTOR)

- 45 mg/0.5 mL (NDC 83457-651-96)
- 90 mg/mL (NDC 83457-652-96)

Single-dose Vial

• 45 mg/0.5 mL (NDC 83457-651-94)

For Intravenous Infusion

Single-dose Vial

• 130 mg/26 mL (5 mg/mL) (NDC 83457-654-94)

Storage and Stability

Store PYZCHIVA vials, prefilled syringes, and prefilled PYZCHIVA AUTOINJECTORs refrigerated between 2°C to 8°C (36°F to 46°F). Store PYZCHIVA vials upright. Keep the product in the original carton to protect from light until the time of use. Do not freeze. Do not shake.

If needed, individual prefilled syringes, and prefilled PYZCHIVA AUTOINJECTORs may be stored at room temperature up to 30°C (86°F) for a maximum single period of up to 35 days in the original carton to protect from light. If not used within 35 days of room temperature storage, discard the prefilled syringe and prefilled PYZCHIVA AUTOINJECTOR. The prefilled syringe, and prefilled PYZCHIVA AUTOINJECTOR may be returned to the refrigerator one time only for a maximum of 60 days. If not used within 60 days, discard the prefilled syringe and prefilled PYZCHIVA AUTOINJECTOR. Record the date when the prefilled syringe, and prefilled PYZCHIVA AUTOINJECTOR are removed from and returned to the refrigerator on the carton in the space provided.

Do not use PYZCHIVA after the expiration date on the carton or on the prefilled syringe.

17 PATIENT COUNSELING INFORMATION

Advise the patient and/or caregiver to read the FDA-approved patient labeling (Medication Guide and Instructions for Use).

Infections

Inform patients that PYZCHIVA may lower the ability of their immune system to fight infections and to contact their healthcare provider immediately if they develop any signs or symptoms of infection [see Warnings and Precautions (5.1)].

Malignancies

Inform patients of the risk of developing malignancies while receiving PYZCHIVA [see Warnings and Precautions (5.4)].

Serious Hypersensitivity and Reactions

- Inform patients that serious hypersensitivity reactions have been reported with intravenous and subcutaneous administration of ustekinumab products. Instruct patients to discontinue Pyzchiva and seek immediate medical attention if they experience any signs or symptoms of hypersensitivity reactions [see Warnings and Precautions (5.5)].

Posterior Reversible Encephalopathy Syndrome (PRES)

Inform patients to immediately contact their healthcare provider if they experience signs and symptoms of PRES (which may include headache, seizures, confusion, or visual disturbances) [see Warnings and Precautions (5.6)].

Immunizations

Inform patients that PYZCHIVA can interfere with the usual response to immunizations and that they should avoid live vaccines [see Warnings and Precautions (5.7)].

Administration

Instruct patients to follow sharps disposal recommendations, as described in the Instructions for Use.

Manufactured by:
Samsung Bioepis Co., Ltd.,
76, Songdogyoyuk-ro, Yeonsu-gu, Incheon, 21987, Republic of Korea
U.S. License No. 2046

Manufactured for:
Cordavis Limited
Dublin, Ireland

MEDICATION GUIDE
PYZCHIVA® (Piz-chi-va)
(ustekinumab-ttwe)
injection, for subcutaneous or intravenous use

What is the most important information I should know about PYZCHIVA?
PYZCHIVA is a medicine that affects your immune system. PYZCHIVA can increase your risk of having serious side effects, including:

- Serious infections: PYZCHIVA may lower the ability of your immune system to fight infections and may increase your risk of infections. Some people have serious infections during treatment with ustekinumab products, including tuberculosis (TB), and infections caused by bacteria, fungi, or viruses. Some people have to be hospitalized for treatment of their infection.
  - Your healthcare provider should check you for TB before starting PYZCHIVA.
  - If your healthcare provider feels that you are at risk for TB, you may be treated with medicine for TB before you begin treatment with PYZCHIVA and during treatment with PYZCHIVA.
  - Your healthcare provider should watch you closely for signs and symptoms of TB while you are being treated with PYZCHIVA.
  You should not start PYZCHIVA if you have any kind of infection unless your healthcare provider says it is okay.
  Before starting PYZCHIVA, tell your healthcare provider if you:
  - think you have an infection or have symptoms of an infection such as:

◦ fever, sweat, or chills
◦ muscle aches
◦ cough
◦ shortness of breath
◦ blood in phlegm

◦ weight loss
◦ warm, red, or painful skin or sores on your body
◦ diarrhea or stomach pain
◦ burning when you urinate or urinate more often than normal
◦ feel very tired

- are being treated for an infection or have any open cuts.
- get a lot of infections or have infections that keep coming back.
- have TB or have been in close contact with someone with TB.

After starting PYZCHIVA, call your healthcare provider right away if you have any symptoms of an infection (see above). These may be signs of infections such as chest infections, or skin infections or shingles that could have serious complications. PYZCHIVA can make you more likely to get infections or make an infection that you have worse.

- People who have a genetic problem where the body does not make any of the proteins interleukin 12 (IL-12) and interleukin 23 (IL-23) are at a higher risk for certain serious infections. These infections can spread throughout the body and cause death. People who take PYZCHIVA may also be more likely to get these infections.
- Cancers. PYZCHIVA may decrease the activity of your immune system and increase your risk for certain types of cancers. Tell your healthcare provider if you have ever had any type of cancer. Some people who are receiving ustekinumab products and have risk factors for skin cancer have developed certain types of skin cancers. During your treatment with PYZCHIVA, tell your healthcare provider if you develop any new skin growths.

What is PYZCHIVA?
PYZCHIVA is a prescription medicine used to treat:

- adults and children 6 years of age and older with moderate to severe plaque psoriasis who may benefit from taking injections or pills (systemic therapy) or phototherapy (treatment using ultraviolet light alone or with pills).
- adults and children 6 years of age and older with active psoriatic arthritis.
- adults with moderately to severely active Crohn's disease.
- adults with moderately to severely active ulcerative colitis.

It is not known if PYZCHIVA is safe and effective in children with Crohn's disease or ulcerative colitis or in children less than 6 years of age with plaque psoriasis or psoriatic arthritis.

Who should not use PYZCHIVA?
Do not use PYZCHIVA if you are allergic to ustekinumab products or any of the ingredients in PYZCHIVA. See the end of this Medication Guide for a complete list of ingredients in PYZCHIVA.

Before you use or receive PYZCHIVA, tell your healthcare provider about all of your medical conditions, including if you:

- have any of the conditions or symptoms listed in the section "What is the most important information I should know about PYZCHIVA?"
- ever had an allergic reaction to ustekinumab products. Ask your healthcare provider if you are not sure.
- have recently received or are scheduled to receive an immunization (vaccine). People who are being treated with PYZCHIVA should avoid receiving live vaccines. Tell your healthcare provider if anyone in your house needs a live vaccine. The viruses used in some types of live vaccines can spread to people with a weakened immune system and can cause serious problems. You should avoid receiving the BCG vaccine during the one year before receiving PYZCHIVA or one year after you stop receiving PYZCHIVA.
- have any new or changing lesions within psoriasis areas or on normal skin.
- are receiving or have received allergy shots, especially for serious allergic reactions. Allergy shots may not work as well for you during treatment with PYZCHIVA. PYZCHIVA may also increase your risk of having an allergic reaction to an allergy shot.
- receive or have received phototherapy for your psoriasis.
- are pregnant or plan to become pregnant. It is not known if PYZCHIVA can harm your unborn baby. You and your healthcare provider should decide if you will receive PYZCHIVA.
- are breastfeeding or plan to breastfeed. PYZCHIVA can pass into your breast milk.
- Talk to your healthcare provider about the best way to feed your baby if you receive PYZCHIVA.

Tell your healthcare provider about all the medicines you take, including prescription and over-the-counter medicines, vitamins, and herbal supplements.
Know the medicines you take. Keep a list of them to show your healthcare provider and pharmacist when you get a new medicine.

How should I use PYZCHIVA?

- Use PYZCHIVA exactly as your healthcare provider tells you to. The healthcare provider will determine the right dose of PYZCHIVA, the amount for each injection, and how often it should be given. Be sure to keep all scheduled follow-up appointments.
- Adults with Crohn's disease and ulcerative colitis will receive the first dose of PYZCHIVA through a vein in the arm (intravenous infusion) in a healthcare facility by a healthcare provider. It takes at least 1 hour to receive the full dose of medicine. PYZCHIVA will then be received as an injection under the skin (subcutaneous injection) 8 weeks after the first dose of PYZCHIVA, as described below.
- Adults and children 6 years of age and older with plaque psoriasis or psoriatic arthritis will receive PYZCHIVA as an injection under the skin as described below.
- Injecting PYZCHIVA under the skin
  - PYZCHIVA is intended for use under the guidance and supervision of a healthcare provider.
  - In children, it is recommended that PYZCHIVA be administered by a healthcare provider. If a healthcare provider decides that you or a caregiver may give the injections of PYZCHIVA at home, you or a caregiver should receive training on the right way to prepare and give the injections.
  - Do not try to inject PYZCHIVA until you have been shown how to give the injections by a healthcare provider.
  - PYZCHIVA can be injected under the skin in the upper arms, buttocks, upper legs (thighs) or stomach area (abdomen).
  - Do not give an injection in an area of the skin that is tender, bruised, red or hard.
  - Use a different injection site each time you use PYZCHIVA.
- If you inject too much PYZCHIVA, call the healthcare provider or Poison Help line at 1-800-222-1222, or go to the nearest emergency room right away.

Read the detailed Instructions for Use at the end of this Medication Guide for instructions about how to prepare and inject a dose of PYZCHIVA, and how to properly throw away (dispose of) used needles, syringes, vials, and PYZCHIVA AUTOINJECTORs. The syringe, needle, vial, and PYZCHIVA AUTOINJECTOR must never be re-used. After the rubber stopper is punctured, PYZCHIVA can become contaminated by harmful bacteria which could cause an infection if re-used. Therefore, throw away any unused portion of PYZCHIVA.

What should I avoid while using PYZCHIVA?
You should avoid receiving a live vaccine during treatment with PYZCHIVA. See "Before you use or receive PYZCHIVA, tell your healthcare provider about all of your medical conditions, including if you:"

What are the possible side effects of PYZCHIVA?
PYZCHIVA may cause serious side effects, including:

- See "What is the most important information I should know about PYZCHIVA?"
- Serious allergic reactions. Serious allergic reactions including death can occur with PYZCHIVA. Stop using PYZCHIVA and get medical help right away if you get any of the following symptoms of a serious allergic reaction:

- feeling faint
- swelling of your face, eyelids, tongue, or throat
- chest discomfort

- trouble breathing
- skin rash

- Posterior Reversible Encephalopathy Syndrome (PRES). PRES is a rare condition that affects the brain and can cause death. Tell your healthcare provider right away if you get any symptoms of PRES during treatment with PYZCHIVA, including:

- headache
- seizures

- confusion
- vision problems

- Lung inflammation. Cases of lung inflammation have happened in some people who receive ustekinumab products, and may be serious. These lung problems may need to be treated in a hospital. Tell your healthcare provider right away if you develop shortness of breath or a cough that doesn't go away during treatment with PYZCHIVA.

The most common side effects of PYZCHIVA include:

- nasal congestion, sore throat, and runny nose
- upper respiratory infections
- fever
- headache
- tiredness
- itching
- nausea and vomiting
- influenza

- redness at the injection site
- vaginal yeast infections
- urinary tract infections
- sinus infection
- bronchitis
- diarrhea
- stomach pain
- joint pain

These are not all of the possible side effects of PYZCHIVA. Call your doctor for medical advice about side effects. You may report side effects to FDA at 1-800-FDA-1088.
You may also report side effects to Cordavis Limited at 1-833-267-3114.

How should I store PYZCHIVA?

- Store PYZCHIVA vials, prefilled syringes, and prefilled PYZCHIVA AUTOINJECTORs in a refrigerator between 36°F to 46°F (2°C to 8°C).
- Store PYZCHIVA vials standing up straight (upright).
- Store PYZCHIVA in the original carton to protect it from light until time to use it.
- Do not freeze PYZCHIVA.
- Do not shake PYZCHIVA.
- If needed, individual PYZCHIVA prefilled syringes, and prefilled PYZCHIVA AUTOINJECTORs may be stored at room temperature up to 86°F (30°C) for a maximum single period of up to 35 days in the original carton to protect from light.
- Record the date when the prefilled syringe and prefilled PYZCHIVA AUTOINJECTOR are first removed from the refrigerator on the carton in the space provided.
- You may return the prefilled syringe and prefilled PYZCHIVA AUTOINJECTOR to the refrigerator 1 time only for a maximum of 60 days, either during the 35-day period or at the end of the 35-day period.
- Record the date when the prefilled syringe and prefilled PYZCHIVA AUTOINJECTOR are returned to the refrigerator on the carton.
- Throw away (discard) the prefilled syringe and prefilled PYZCHIVA AUTOINJECTOR if not used within 35 days of room temperature storage and you did not return it to the refrigerator, or if it has been returned to the refrigerator and is not used within 60 days.
- Do not use PYZCHIVA after the expiration date on the carton or on the prefilled syringe and prefilled PYZCHIVA AUTOINJECTOR.

Keep PYZCHIVA and all medicines out of the reach of children.

General information about the safe and effective use of PYZCHIVA.
Medicines are sometimes prescribed for purposes other than those listed in a Medication Guide. Do not use PYZCHIVA for a condition for which it was not prescribed. Do not give PYZCHIVA to other people, even if they have the same symptoms that you have. It may harm them. You can ask your pharmacist or healthcare provider for information about PYZCHIVA that was written for health professionals.

What are the ingredients in PYZCHIVA?
Active ingredient: ustekinumab-ttwe

Inactive ingredients: Single-dose prefilled syringe, single-dose vial, and single-dose prefilled PYZCHIVA AUTOINJECTOR for subcutaneous use contain histidine, histidine hydrochloride monohydrate, polysorbate 80, and sucrose. Single-dose vial for intravenous infusion contains edetate disodium, histidine, histidine hydrochloride monohydrate, methionine, polysorbate 80, and sucrose.

Manufactured by: Samsung Bioepis Co., Ltd.,
76, Songdogyoyuk-ro, Yeonsu-gu, Incheon, 21987, Republic of Korea
U.S. License No. 2046
Manufactured for: Cordavis Limited

Dublin, Ireland
For more information, call 1-833-267-3114.

This Medication Guide has been approved by the U.S. Food and Drug Administration.

Revised: 02/2026

INSTRUCTIONS FOR USE

PYZCHIVA® (Piz-chi-va)
(ustekinumab-ttwe)
injection, for subcutaneous use

This Instructions for Use contains information on how to inject PYZCHIVA using a prefilled syringe.

Read this Instructions for Use before you start using PYZCHIVA. A healthcare provider should show you how to prepare and give an injection of PYZCHIVA the right way.

If you cannot give the injection:

- ask a healthcare provider to help you, or
- ask someone who has been trained by a healthcare provider to give the injections.

Do not try to inject PYZCHIVA until you have been shown how to inject PYZCHIVA by a healthcare provider.

Important information You Need to Know Before Injecting PYZCHIVA:

- For subcutaneous use only (inject directly under the skin)
- Before you start, check the carton to make sure that it is the right dose. You will have either 45 mg or 90 mg as prescribed by the healthcare provider.
  - If the dose is 45 mg, you will receive one 45 mg prefilled syringe.
  - If the dose is 90 mg, you will receive either one 90 mg prefilled syringe or two 45 mg prefilled syringes. If you receive two 45 mg prefilled syringes for a 90 mg dose, you will need to give two injections, one right after the other.
- Check the expiration date on the prefilled syringe and carton. Do not use PYZCHIVA after the expiration date has passed, or if the prefilled syringe has been stored above 86°F (30°C), stored at room temperature up to 86°F (30°C) for longer than 35 days, or returned to the refrigerator and stored for longer than 60 days. Call the healthcare provider or pharmacist, or call Cordavis Limited at 1-833-267-3114 for help.
- Make sure the syringe is not damaged. Do not use the prefilled syringe if it is damaged.
- Check the prefilled syringe for any particles or discoloration. The liquid in the prefilled syringe should look clear and colorless to light yellow.
- Do not use if it is frozen, discolored, cloudy or has particles. Get a new prefilled syringe.
- Do not shake the prefilled syringe at any time. Shaking the prefilled syringe may damage the PYZCHIVA medicine. If the prefilled syringe has been shaken, do not use it. Get a new prefilled syringe.
- To reduce the risk of accidental needle sticks, each prefilled syringe has a needle guard that is automatically activated to cover the needle after you have given the injection. Do not pull back on the plunger at any time.

Storing PYZCHIVA prefilled syringes

- Store PYZCHIVA prefilled syringes in the refrigerator between 36°F to 46°F (2°C to 8°C).
- Store PYZCHIVA prefilled syringes in the original carton to protect from light until the time of use.
- Do not freeze PYZCHIVA prefilled syringes.
- If needed, individual prefilled syringes may be stored at room temperature up to 86°F (30°C) for a maximum single period of up to 35 days in the original carton to protect from light.
- Record the date when the prefilled syringe is removed from the refrigerator on the carton in the space provided.
- You may return the prefilled syringe to the refrigerator 1 time only for a maximum of 60 days, either during the 35-day period or at the end of the 35-day period.
- Record the date when the prefilled syringe is returned to the refrigerator on the carton.
- Throw away (discard) the prefilled syringe if not used within 35 days of room temperature storage and you did not return it to the refrigerator, or if it has been returned to the refrigerator and is not used within 60 days.

Keep PYZCHIVA and all medicines out of the reach of children.

Gather the supplies you will need to prepare and to give the injection. (See Figure A)
You will need:

- antiseptic wipes
- cotton balls or gauze pads
- adhesive bandage
- your prescribed dose of PYZCHIVA (See Figure B)
- FDA-cleared sharps disposal container. See "Step 4: Disposing of the syringes."

Figure A

Figure B

Step 1: Preparing the injection

- Choose a well-lit, clean, flat work surface.
- Leave PYZCHIVA prefilled syringe at room temperature for about 30 minutes before injecting. Do not warm the prefilled syringe in any other way (for example, do not warm it in a microwave or in hot water).
- Wash your hands well with soap and warm water.
- Hold the prefilled syringe with the covered needle pointing upward.

Step 2: Prepare the injection site

- Choose an injection site around the stomach area (abdomen), buttocks, upper legs (thighs). If a caregiver is giving the injection, the outer area of the upper arms may also be used. (See Figure C)
- Use a different injection site for each injection. Do not give an injection in an area of the skin that is tender, bruised, red or hard.
- Clean the skin with an antiseptic wipe where you plan to give the injection.
- Do not touch this area again before giving the injection. Let the skin dry before injecting.
- Do not fan or blow on the clean area.

Figure C

*Areas in gray are recommended injection sites.
Step 3: Injecting PYZCHIVA

- Remove the needle cover when you are ready to inject PYZCHIVA.
- Do not touch the plunger or plunger head while removing the needle cover.
- Hold the body of the prefilled syringe with one hand, and pull the needle cover straight off. (See Figure D)
- Put the needle cover in the trash.
- You may also see a drop of liquid at the end of the needle. This is normal.
- Do not touch the needle or let it touch anything.
- Do not use the prefilled syringe if it is dropped without the needle cover in place.

Figure D

- Hold the body of the prefilled syringe in one hand between the thumb and index fingers. (See Figure E)

Figure E

- Do not pull back on the plunger at any time.
- Use the other hand to gently pinch the cleaned area of skin. Hold firmly.
- Use a quick, dart-like motion to insert the needle into the pinched skin at about a 45-degree angle. (See Figure F)

Figure F

- Inject all of the liquid by using your thumb to push in the plunger until the plunger head is completely between the needle guard wings. (See Figure G)

Figure G

- When the plunger is pushed as far as it will go, keep pressure on the plunger head. Take the needle out of the skin and then let go of the skin.
- Slowly take your thumb off the plunger head. This will let the empty syringe move up until the entire needle is covered by the needle guard. (See Figure H)

Figure H

- When the needle is pulled out of the skin, there may be a little bleeding at the injection site. This is normal. You can press a cotton ball or gauze pad to the injection site if needed. Do not rub the injection site. You may cover the injection site with a small adhesive bandage, if necessary.

If the dose is 90 mg, you will receive either one 90 mg prefilled syringe or two 45 mg prefilled syringes. If you receive two 45 mg prefilled syringes for a 90 mg dose, you will need to give a second injection right after the first. Repeat Steps 1 to 3 for the second injection using a new syringe. Choose a different site for the second injection.

Step 4: Disposing of the syringes.

- Put the syringe in an FDA-cleared sharps disposal container right away after use. Do not throw away (dispose of) syringes in your household trash.
- If you do not have an FDA-cleared sharps disposal container, you may use a household container that is:
  - made of heavy-duty plastic,
  - can be closed with a tight-fitting, puncture-resistant lid, without sharps being able to come out,
  - upright and stable during use,
  - leak-resistant,
  - and properly labeled to warn of hazardous waste inside the container.
- When your sharps disposal container is almost full, you will need to follow your community guidelines for the right way to dispose of your sharps disposal container. There may be local or state laws about how to throw away syringes and needles. For more information about safe sharps disposal, and for specific information about sharps disposal in the state that you live in, go to the FDA's website at: http://www.fda.gov/safesharpsdisposal.
- Do not dispose of your sharps disposal container in your household trash unless your community guidelines permit this. Do not recycle your sharps disposal container.
- If you have any questions, talk to your healthcare provider or pharmacist.

Manufactured by:
Samsung Bioepis Co., Ltd.,
76, Songdogyoyuk-ro, Yeonsu-gu, Incheon, 21987, Republic of Korea
U.S. License No. 2046

Manufactured for:
Cordavis Limited
Dublin, Ireland

This Instructions for Use has been approved by the U.S. Food and Drug Administration. Revised: 02/2026

INSTRUCTIONS FOR USE

PYZCHIVA® (Piz-chi-va)
(ustekinumab-ttwe)
injection, for subcutaneous use

This Instructions for Use contains information on how to inject PYZCHIVA using a vial.

Read this Instructions for Use before you start using PYZCHIVA. A healthcare provider should show you how to prepare, measure the dose, and give an injection of PYZCHIVA the right way.

If you cannot give the injection:

- ask a healthcare provider to help you, or
- ask someone who has been trained by a healthcare provider to give the injections.

Do not try to inject PYZCHIVA until you have been shown how to inject PYZCHIVA by a healthcare provider.

Important information You Need to Know Before Injecting PYZCHIVA:

- For subcutaneous use only (inject directly under the skin)
- Before you start, check the carton to make sure that it is the right dose. You will have either 45 mg or 90 mg as prescribed by the healthcare provider.
  - If the dose is 45 mg or less you will receive one 45 mg vial.
  - If the dose is 90 mg, you will receive two 45 mg vials and you will need to give two injections, one right after the other.
- Check the expiration date on the vial and carton. If the expiration date has passed, do not use it. If the expiration date has passed, call the healthcare provider or pharmacist, or call Cordavis Limited at 1-833-267-3114 for help.
- Check the vial for any particles or discoloration. The liquid in the vial should look clear and colorless to light yellow.
- Do not use if it is frozen, discolored, cloudy or has particles. Get a new vial.
- Do not shake the vial at any time. Shaking the vial may damage the PYZCHIVA medicine. If the vial has been shaken, do not use it. Get a new vial.
- Do not use a PYZCHIVA vial more than one time, even if there is medicine left in the vial. After the rubber stopper is punctured, PYZCHIVA can become contaminated by harmful bacteria which could cause an infection if re-used. Therefore, throw away any unused PYZCHIVA after you give the injection.
- Safely throw away (dispose of) PYZCHIVA vials, needles, and syringes after use. See "Step 6: Disposing of needles, syringes, and vials."
- Do not re-use syringes or needles.
- To avoid needle-stick injuries, do not recap needles.

Storing PYZCHIVA vials

- Store PYZCHIVA vials in a refrigerator between 36°F to 46°F (2°C to 8°C).
- Store PYZCHIVA vials standing up straight (upright).
- Store PYZCHIVA vials in the original carton to protect from light until the time of use.
- Do not freeze PYZCHIVA vials.

Keep PYZCHIVA and all medicines out of the reach of children.

Gather the supplies you will need to prepare PYZCHIVA and to give the injection. (See Figure A)

You will need:

- a syringe with the needle attached, you will need a prescription from a healthcare provider to get syringes with the needles attached from a pharmacy.
- antiseptic wipes
- cotton balls or gauze pads
- adhesive bandage
- your prescribed dose of PYZCHIVA
- FDA-cleared sharps disposal container. See "Step 6: Disposing of needles, syringes, and vials."

Figure A

Step 1: Preparing the injection.

- Choose a well-lit, clean, flat work surface.
- Wash your hands well with soap and warm water.

Step 2: Preparing your injection site

- Choose an injection site around the stomach area (abdomen), buttocks, and upper legs (thighs).
- If a caregiver is giving the injection, the outer area of the upper arms may also be used. (See Figure B)
- Use a different injection site for each injection. Do not give an injection in an area of the skin that is tender, bruised, red or hard.
- Clean the skin with an antiseptic wipe where you plan to give the injection.
- Do not touch this area again before giving the injection. Let the skin dry before injecting.
- Do not fan or blow on the clean area.

Figure B

*Areas in gray are recommended injection sites.

Step 3: Preparing the vial.

- Remove the cap from the top of the vial. Throw away the cap but do not remove the rubber stopper. (See Figure C)

Figure C

- Clean the rubber stopper with an antiseptic wipe. (See Figure D)

Figure D

- Do not touch the rubber stopper after you clean it.
- Put the vial on a flat surface.

Step 4: Preparing the syringe

- Pick up the syringe with the needle attached.
- Remove the cap that covers the needle. (See Figure E)
- Throw the needle cap away. Do not touch the needle or allow the needle to touch anything.

Figure E

- Carefully pull back on the plunger to the line that matches the dose prescribed by the healthcare provider.
- Hold the vial between your thumb and index (pointer) finger.
- Use your other hand to push the syringe needle through the center of the rubber stopper. (See Figure F)

Figure F

- Push down on the plunger until all of the air has gone from the syringe into the vial.
- Turn the vial and the syringe upside down. (See Figure G)
- Hold the PYZCHIVA vial with one hand.
- It is important that the needle is always in the liquid in order to prevent air bubbles forming in the syringe.
- Pull back on the syringe plunger with your other hand.
- Fill the syringe until the black tip of the plunger lines up with the mark that matches the prescribed dose.

Figure G

- Do not remove the needle from the vial. Hold the syringe with the needle pointing up to see if it has any air bubbles inside.
- If there are air bubbles, gently tap the side of the syringe until the air bubbles rise to the top. (See Figure H)
- Slowly press the plunger up until all of the air bubbles are out of the syringe (but none of the liquid is out).
- Remove the syringe from the vial. Do not lay the syringe down or allow the needle to touch anything.

Figure H

Step 5: Injecting PYZCHIVA

- Hold the barrel of the syringe in one hand, between the thumb and index fingers.
- Do not pull back on the plunger at any time.
- Use the other hand to gently pinch the cleaned area of skin. Hold firmly.
- Use a quick, dart-like motion to insert the needle into the pinched skin at about a 45-degree angle. (See Figure I)

Figure I

- Push the plunger with your thumb as far as it will go to inject all of the liquid. Push it slowly and evenly, keeping the skin gently pinched.
- When the syringe is empty, pull the needle out of the skin and then let go of the skin. (See Figure J)

Figure J

- When the needle is pulled out of the skin, there may be a little bleeding at the injection site. This is normal. You can press a cotton ball or gauze pad to the injection site if needed. Do not rub the injection site. You may cover the injection site with a small adhesive bandage, if necessary.

If the dose is 90 mg, you will receive two 45 mg vials and you will need to give a second injection right after the first. Repeat Steps 1 to 5 using a new syringe. Choose a different site for the second injection.

Step 6: Disposing of needles, syringes, and vials.

- Do not re-use a syringe or needle.
- To avoid needle-stick injuries, do not recap a needle.
- Put the needles and syringes in an FDA-cleared sharps disposal container right away after use. Do not throw away (dispose of) needles and syringes in your household trash.
- If you do not have an FDA-cleared sharps disposal container, you may use a household container that is:
  - made of heavy-duty plastic
  - can be closed with a tight-fitting, puncture-resistant lid, without sharps being able to come out
  - upright and stable during use
  - leak-resistant,
  - and properly labeled to warn of hazardous waste inside the container.
- When your sharps disposal container is almost full, you will need to follow your community guidelines for the right way to dispose of your sharps disposal container. There may be local or state laws about how to throw away syringes and needles. For more information about safe sharps disposal, and for specific information about sharps disposal in the state that you live in, go to the FDA's website at: http://www.fda.gov/safesharpsdisposal.
- Do not dispose of your sharps disposal container in your household trash unless your community guidelines permit this. Do not recycle your sharps disposal container.
- Throw away the vial into the container where you put the syringes and needles.
- If you have any questions, talk to your healthcare provider or pharmacist.

Manufactured by:
Samsung Bioepis Co., Ltd.,
76, Songdogyoyuk-ro, Yeonsu-gu, Incheon, 21987, Republic of Korea
U.S. License No. 2046

Manufactured for:
Cordavis Limited
Dublin, Ireland

This Instructions for Use has been approved by the U.S. Food and Drug Administration. Revised: 02/2026

INSTRUCTIONS FOR USE

PYZCHIVA® (Piz-chi-va) AUTOINJECTOR
(ustekinumab-ttwe)
injection, for subcutaneous use

This Instructions for Use contains information on how to inject PYZCHIVA using a 45 mg/0.5 mL single-dose prefilled autoinjector (PYZCHIVA AUTOINJECTOR).
Read this Instructions for Use before you start using PYZCHIVA AUTOINJECTOR. A healthcare provider should show you how to prepare and give the injection the right way.
If you cannot give the injection:

- ask a healthcare provider to help you, or
- ask someone who has been trained by a healthcare provider to give the injections.

Do not try to inject PYZCHIVA until you have been shown the right way to give the injections by a healthcare provider.

Guide to parts:

Figure A

Important information You Need to Know Before Injecting PYZCHIVA

- For subcutaneous injection only (inject directly under the skin)
- Do not remove the needle cap before you are ready to inject.
- Do not shake the PYZCHIVA AUTOINJECTOR at any time. Shaking the PYZCHIVA AUTOINJECTOR may damage the PYZCHIVA medicine. If the PYZCHIVA AUTOINJECTOR has been shaken, do not use it. Get a new PYZCHIVA AUTOINJECTOR.
- Check the expiration date on the PYZCHIVA AUTOINJECTOR and carton. Do not use PYZCHIVA after the expiration date has passed, or if the PYZCHIVA AUTOINJECTOR has been stored above 86°F (30°C), stored at room temperature up to 86°F (30°C) for longer than 35 days, or returned to the refrigerator and stored longer than 60 days. Call the healthcare provider or pharmacist, or call 1-833-267-3114 for help.
- Make sure the PYZCHIVA AUTOINJECTOR is not damaged. Do not use the PYZCHIVA AUTOINJECTOR if it is damaged.
- Check the PYZCHIVA AUTOINJECTOR for any particles or discoloration. The liquid (medicine) in the PYZCHIVA AUTOINJECTOR should look clear and colorless to light yellow.
- Do not use if it is frozen, discolored, cloudy or has particles. Get a new PYZCHIVA AUTOINJECTOR.

Storing PYZCHIVA AUTOINJECTOR:

- Store PYZCHIVA AUTOINJECTOR in the refrigerator between 36°F to 46°F (2°C to 8°C).
- Store PYZCHIVA AUTOINJECTOR in the original carton to protect from light or physical damage.
- Do not freeze PYZCHIVA AUTOINJECTOR.
- If needed, PYZCHIVA AUTOINJECTOR may be stored at room temperature up to 86°F (30°C) for a maximum single period of up to 35 days.
- The PYZCHIVA AUTOINJECTOR can be returned to the refrigerator during the 35-day period or at the end of the 35-day period.
- You may return the PYZCHIVA AUTOINJECTOR to the refrigerator 1 time only for a maximum of 60 days.
- Record the date when the PYZCHIVA AUTOINJECTOR is removed from and returned to the refrigerator on the carton in the space provided.
- Discard the PYZCHIVA AUTOINJECTOR if not used within 35 days of room temperature storage and you did not return it to the refrigerator, or if it has been returned to the refrigerator and is not used within 60 days.

Preparing to Inject PYZCHIVA AUTOINJECTOR

Step 1: Before you start, check the carton to make sure that it is the right dose. You will have a PYZCHIVA AUTOINJECTOR that contains 45 mg of PYZCHIVA as prescribed by the healthcare provider.

- If the dose is 45 mg, you will receive one 45 mg PYZCHIVA AUTOINJECTOR.
- If the dose is 90 mg, you will receive two 45 mg PYZCHIVA AUTOINJECTOR. If you receive two 45 mg PYZCHIVA AUTOINJECTOR for a 90 mg dose, you will need to give two injections, one right after the other.

Step 2: Gather supplies

- Choose a well-lit, clean, flat work surface.
- Gather the supplies you will need to prepare and to give the injection (Figure B).
- You will need:
  - alcohol swab
  - cotton balls or gauze pads
  - adhesive bandage
  - the prescribed dose of PYZCHIVA
  - FDA-cleared sharps disposal container. (See "Disposing of PYZCHIVA AUTOINJECTOR.")

Figure B

Step 3: Inspect the PYZCHIVA AUTOINJECTOR (Figure C)

- Check the expiration date on the PYZCHIVA AUTOINJECTOR or carton.
- Check the medicine in the viewing window for any particles or discoloration. The medicine should look clear and colorless to light yellow.
- Make sure the PYZCHIVA AUTOINJECTOR is not damaged.
- Do not use the PYZCHIVA AUTOINJECTOR if:
  - the expiration date has passed or if the PYZCHIVA AUTOINJECTOR has been kept at room temperature up to 86°F (30°C) for longer than a maximum single period of 35 days or if the prefilled autoinjector has been stored above 86°F (30°C).
  - the medicine is frozen, discolored, cloudy or has particles.
  - it is damaged.
  - it is dropped and appears cracked or broken.
- It is normal to see 1 or more bubbles in the viewing window.
- It is normal to see the yellow indicator partially visible in the viewing window.

Figure C

Step 4: Allow the medicine to reach room temperature

- Leave the PYZCHIVA AUTOINJECTOR at room temperature for about 30 minutes before injecting after removing it from the refrigerator.
- Do not warm the PYZCHIVA AUTOINJECTOR in any other way (for example, do not warm it in a microwave or in hot water).

Step 5: Wash your hands

- Wash your hands well with soap and warm water (Figure D).

Figure D

Step 6: Choose the injection site

- Choose an injection site around the stomach area (abdomen), buttocks, upper legs (thighs). If a caregiver is giving you the injection, the outer area of the upper arms may also be used. (Figure E)
- Use a different injection site for each injection.
- Do not give an injection in an area of the skin that is tender, bruised, red, or hard.

Figure E
*Areas in gray are the recommended injection sites.

Step 7: Clean the skin at the injection site

- Clean the skin where you plan to give the injection with a new alcohol swab. (Figure F)
- Do not touch this area again before giving the injection. Let the skin dry before injecting.
- Do not fan or blow on the clean area.

Figure F

Injecting PYZCHIVA AUTOINJECTOR

Step 8: Pull the needle cap straight off when you are ready to inject the PYZCHIVA AUTOINJECTOR (Figure G).

- Throw away the needle cap.
- It is normal to see a few drops of liquid come out of the needle.
- Do not twist or bend the needle cap while removing it, as this may damage the needle.
- Do not touch the yellow needle guard.
- Do not use the PYZCHIVA AUTOINJECTOR if it is dropped after removing the needle cap. Call your healthcare provider for instructions.

Figure G

Step 9: Place the PYZCHIVA AUTOINJECTOR straight on the skin at a 90-degree angle (Figure H).

- Make sure that the PYZCHIVA AUTOINJECTOR is positioned so that you can clearly see the viewing window.

Figure H

Step 10: Firmly push the PYZCHIVA AUTOINJECTOR down onto the skin to start the injection (Figure I).

- You will hear a first click when the injection begins.

Figure I

Step 11: Continue to press down onto the skin until the yellow indicator stops moving and you hear a second click. (Figure J).

- Do not release pressure against the injection site before the injection is complete.
- Do not move the PYZCHIVA AUTOINJECTOR during the injection.
- The injection could take up to 10 seconds.
- Check that the viewing window has turned yellow to make sure that the full dose has been delivered. A small gray band may still be visible in the viewing window.

Figure J

Step 12: Remove the empty PYZCHIVA AUTOINJECTOR from the skin (Figure K).

- The yellow needle guard will completely cover the needle.
- Do not put the needle cap back on the PYZCHIVA AUTOINJECTOR.
- When the needle is pulled out of the skin, there may be a little bleeding or a few drops at the injection site. This is normal. You can press a cotton ball or gauze pad to the injection site if needed. Do not rub the injection site. You may cover the injection site with a small adhesive bandage, if necessary.

Figure K

If the dose is 90 mg, you will receive two 45 mg PYZCHIVA AUTOINJECTORs and you will need to give a second injection right after the first. Repeat Steps 1 to 12 for the second injection using a new PYZCHIVA AUTOINJECTOR. Choose a different site for the second injection.

Step 13: Disposing of PYZCHIVA AUTOINJECTOR

- Put the used PYZCHIVA AUTOINJECTOR in an FDA-cleared sharps disposal container right away after use (Figure L).
- Do not throw away (dispose of) PYZCHIVA AUTOINJECTORs in your household trash.

Figure L

- If you do not have an FDA-cleared sharps disposal container, you may use a household container that is:
  - made of heavy-duty plastic,
  - can be closed with a tight-fitting, puncture-resistant lid, without sharps being able to come out,
  - upright and stable during use,
  - leak-resistant,
  - and properly labeled to warn of hazardous waste inside the container.
- When your sharps disposal container is almost full, you will need to follow your community guidelines for the right way to dispose of your sharps disposal container. There may be local or state laws about how to throw away autoinjectors and needles. For more information about safe sharps disposal, and for specific information about sharps disposal in the state that you live in, go to the FDA's website at: http://www.fda.gov/safesharpsdisposal.
- Do not dispose of your sharps disposal container in your household trash unless your community guidelines permit this. Do not recycle your sharps disposal container.
- If you have any questions, talk to your healthcare provider or pharmacist.

Keep PYZCHIVA and all medicines out of the reach of children.

Manufactured by:
Samsung Bioepis Co., Ltd.,
76, Songdogyoyuk-ro, Yeonsu-gu, Incheon, 21987, Republic of Korea
U.S. License No. 2046

Manufactured for:
Cordavis Limited
Dublin, Ireland

This Instructions for Use has been approved by the U.S. Food and Drug Administration. Revised 02/2026

INSTRUCTIONS FOR USE

PYZCHIVA® (Piz-chi-va) AUTOINJECTOR
(ustekinumab-ttwe)
injection, for subcutaneous use

This Instructions for Use contains information on how to inject PYZCHIVA using a 90 mg/mL single-dose prefilled autoinjector (PYZCHIVA AUTOINJECTOR).
Read this Instructions for Use before you start using PYZCHIVA AUTOINJECTOR. A healthcare provider should show you how to prepare and give the injection the right way.

If you cannot give the injection:

- ask a healthcare provider to help you, or
- ask someone who has been trained by a healthcare provider to give the injections.

Do not try to inject PYZCHIVA until you have been shown the right way to give the injections by a healthcare provider.

Guide to parts:

Figure A

Important information You Need to Know Before Injecting PYZCHIVA

- For subcutaneous injection only (inject directly under the skin)
- Do not remove the needle cap before you are ready to inject.
- Do not shake the PYZCHIVA AUTOINJECTOR at any time. Shaking the PYZCHIVA AUTOINJECTOR may damage the PYZCHIVA medicine. If the PYZCHIVA AUTOINJECTOR has been shaken, do not use it. Get a new PYZCHIVA AUTOINJECTOR.
- Check the expiration date on the PYZCHIVA AUTOINJECTOR and carton. Do not use PYZCHIVA after the expiration date has passed, or if the PYZCHIVA AUTOINJECTOR has been stored above 86°F (30°C), stored at room temperature up to 86°F (30°C) for longer than 35 days, or returned to the refrigerator and stored longer than 60 days. Call the healthcare provider or pharmacist, or call 1-833-267-3114 for help.
- Make sure the PYZCHIVA AUTOINJECTOR is not damaged. Do not use the PYZCHIVA AUTOINJECTOR if it is damaged.
- Check the PYZCHIVA AUTOINJECTOR for any particles or discoloration. The liquid (medicine) in the PYZCHIVA AUTOINJECTOR should look clear and colorless to light yellow.
- Do not use if it is frozen, discolored, cloudy or has particles. Get a new PYZCHIVA AUTOINJECTOR.

Storing PYZCHIVA AUTOINJECTOR:

- Store PYZCHIVA AUTOINJECTOR in the refrigerator between 36°F to 46°F (2°C to 8°C).
- Store PYZCHIVA AUTOINJECTOR in the original carton to protect from light or physical damage.
- Do not freeze PYZCHIVA AUTOINJECTOR.
- If needed, PYZCHIVA AUTOINJECTOR may be stored at room temperature up to 86°F (30°C) for a maximum single period of up to 35 days.
- The PYZCHIVA AUTOINJECTOR can be returned to the refrigerator during the 35-day period or at the end of the 35-day period.
- You may return the PYZCHIVA AUTOINJECTOR to the refrigerator 1 time only for a maximum of 60 days.
- Record the date when the PYZCHIVA AUTOINJECTOR is removed from and returned to the refrigerator on the carton in the space provided.
- Discard the PYZCHIVA AUTOINJECTOR if not used within 35 days of room temperature storage and you did not return it to the refrigerator, or if it has been returned to the refrigerator and is not used within 60 days.

Preparing to Inject PYZCHIVA AUTOINJECTOR

Step 1: Before you start, check the carton to make sure that it is the right dose. You will have a PYZCHIVA AUTOINJECTOR that contains 90 mg of PYZCHIVA as prescribed by the healthcare provider.

Step 2: Gather supplies

- Choose a well-lit, clean, flat work surface.
- Gather the supplies you will need to prepare and to give the injection (Figure B).
- You will need:
  - alcohol swab
  - cotton balls or gauze pads
  - adhesive bandage
  - the prescribed dose of PYZCHIVA
  - FDA-cleared sharps disposal container. (See "Disposing of PYZCHIVA AUTOINJECTOR.")

Figure B
Step 3: Inspect the PYZCHIVA AUTOINJECTOR (Figure C)

- Check the expiration date on the PYZCHIVA AUTOINJECTOR or carton.
- Check the medicine in the viewing window for any particles or discoloration. The medicine should look clear and colorless to light yellow.
- Make sure the PYZCHIVA AUTOINJECTOR is not damaged.
- Do not use the PYZCHIVA AUTOINJECTOR if:
  - the expiration date has passed or if the PYZCHIVA AUTOINJECTOR has been kept at room temperature up to 86°F (30°C) for longer than a maximum single period of 35 days or if the prefilled autoinjector has been stored above 86°F (30°C).
  - the medicine is frozen, discolored, cloudy or has particles.
  - it is damaged.
  - it is dropped and appears cracked or broken.
- It is normal to see 1 or more bubbles in the viewing window.

Figure C

Step 4: Allow the medicine to reach room temperature

- Leave the PYZCHIVA AUTOINJECTOR at room temperature for about 30 minutes before injecting after removing it from the refrigerator.
- Do not warm the PYZCHIVA AUTOINJECTOR in any other way (for example, do not warm it in a microwave or in hot water).

Step 5: Wash your hands

- Wash your hands well with soap and warm water (Figure D).

Figure D

Step 6: Choose the injection site

- Choose an injection site around the stomach area (abdomen), buttocks, upper legs (thighs). If a caregiver is giving you the injection, the outer area of the upper arms may also be used. (Figure E)
- Use a different injection site for each injection.
- Do not give an injection in an area of the skin that is tender, bruised, red, or hard.

Figure E
*Areas in gray are the recommended injection sites.

Step 7: Clean the skin at the injection site

- Clean the skin where you plan to give the injection with a new alcohol swab. (Figure F)
- Do not touch this area again before giving the injection. Let the skin dry before injecting.
- Do not fan or blow on the clean area.

Figure F

Injecting PYZCHIVA AUTOINJECTOR

Step 8: Pull the needle cap straight off when you are ready to inject the PYZCHIVA (Figure G).

- Throw away the needle cap.
- It is normal to see a few drops of liquid come out of the needle.
- Do not twist or bend the needle cap while removing it, as this may damage the needle.
- Do not touch the yellow needle guard.
- Do not use the PYZCHIVA AUTOINJECTOR if it is dropped after removing the needle cap. Call your healthcare provider for instructions.

Figure G
Step 9: Place the PYZCHIVA AUTOINJECTOR straight on the skin at a 90-degree angle (Figure H).

- Make sure that the PYZCHIVA AUTOINJECTOR is positioned so that you can clearly see the viewing window.

Figure H

Step 10: Firmly push the PYZCHIVA AUTOINJECTOR down onto the skin to start the injection (Figure I).

- You will hear a first click when the injection begins.

Figure I

Step 11: Continue to press down onto the skin until the yellow indicator stops moving and you hear a second click. (Figure J).

- Do not release pressure against the injection site before the injection is complete.
- Do not move the PYZCHIVA AUTOINJECTOR during the injection.
- The injection could take up to 10 seconds.
- Check that the viewing window has turned yellow to make sure that the full dose has been delivered. A small gray band may still be visible in the viewing window.

Figure J

Step 12: Remove the empty PYZCHIVA AUTOINJECTOR from the skin (Figure K).
• The yellow needle guard will completely cover the needle.
• Do not put the needle cap back on the PYZCHIVA AUTOINJECTOR.
• When the needle is pulled out of the skin, there may be a little bleeding or a few drops at the injection site. This is normal. You can press a cotton ball or gauze pad to the injection site if needed. Do not rub the injection site. You may cover the injection site with a small adhesive bandage, if necessary.

Figure K

Step 13: Disposing of PYZCHIVA AUTOINJECTOR

- Put the used PYZCHIVA AUTOINJECTOR in an FDA-cleared sharps disposal container right away after use (Figure L).
- Do not throw away (dispose of) PYZCHIVA AUTOINJECTORs in your household trash.

Figure L

- If you do not have an FDA-cleared sharps disposal container, you may use a household container that is:
  - made of heavy-duty plastic,
  - can be closed with a tight-fitting, puncture-resistant lid, without sharps being able to come out,
  - upright and stable during use,
  - leak-resistant,
  - and properly labeled to warn of hazardous waste inside the container.
- When your sharps disposal container is almost full, you will need to follow your community guidelines for the right way to dispose of your sharps disposal container. There may be local or state laws about how to throw away autoinjectors and needles. For more information about safe sharps disposal, and for specific information about sharps disposal in the state that you live in, go to the FDA's website at: http://www.fda.gov/safesharpsdisposal.
- Do not dispose of your sharps disposal container in your household trash unless your community guidelines permit this. Do not recycle your sharps disposal container.
- If you have any questions, talk to your healthcare provider or pharmacist.

Keep PYZCHIVA and all medicines out of the reach of children.

Manufactured by:
Samsung Bioepis Co., Ltd.,
76, Songdogyoyuk-ro, Yeonsu-gu, Incheon, 21987, Republic of Korea
U.S. License No. 2046

Manufactured for:
Cordavis Limited
Dublin, Ireland

This Instructions for Use has been approved by the U.S. Food and Drug Administration. Revised 02/2026

45 mg Carton Label

NDC 83457-651-01

Pyzchiva® 45 mg/0.5 mL
(ustekinumab-ttwe)
Injection
For subcutaneous use

Contains one 45 mg/0.5 mL syringe
Single-dose prefilled syringe - Discard unused portion

Recommended Dosage: See Prescribing Information

ATTENTION: Dispense the enclosed

Medication Guide to each patient.

Cordavis
Rx only

45 mg Carton Label

NDC 83457-651-96
Pyzchiva® autoinjector 45 mg/0.5 mL
(ustekinumab-ttwe)
Injection
For subcutaneous use
Single-dose Prefilled Autoinjector
Contains one 45 mg/0.5 mL autoinjector
Single-dose prefilled autoinjector- Discard unused portion
Recommended Dosage: See Prescribing Information
See enclosed Instructions for Use for how to use your Pyzchiva autoinjector.
ATTENTION: Dispense the enclosed Medication Guide to each patient.
Cordavis
Rx only

90 mg Carton Label

NDC 83457-652-01
Pyzchiva® 90 mg/mL
(ustekinumab-ttwe)
Injection
For subcutaneous use
Contains one 90 mg/mL syringe
Single-dose prefilled syringe - Discard unused portion
Recommended Dosage: See Prescribing Information
ATTENTION: Dispense the enclosed
Medication Guide to each patient.
Cordavis
Rx only

90 mg Carton Label

NDC 83457-652-96
Pyzchiva® autoinjector 90 mg/mL
(ustekinumab-ttwe)
Injection
For subcutaneous use
Single-dose Prefilled Autoinjector
Contains one 90 mg/mL autoinjector
Single-dose prefilled autoinjector- Discard unused portion
Recommended Dosage: See Prescribing Information
See enclosed Instructions for Use for how to use your Pyzchiva autoinjector.
ATTENTION: Dispense the enclosed Medication Guide to each patient.
Cordavis
Rx only